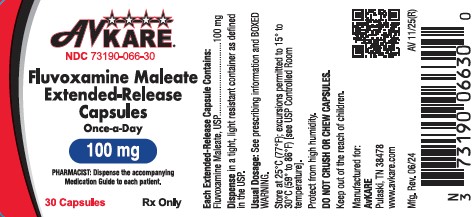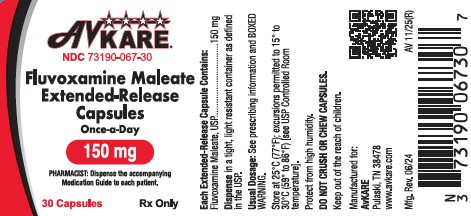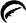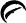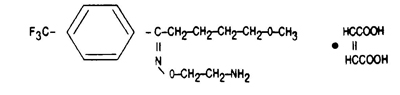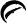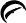 DRUG LABEL: Fluvoxamine Maleate
NDC: 73190-066 | Form: CAPSULE, EXTENDED RELEASE
Manufacturer: AvKARE
Category: prescription | Type: HUMAN PRESCRIPTION DRUG LABEL
Date: 20251204

ACTIVE INGREDIENTS: FLUVOXAMINE MALEATE 100 mg/1 1
INACTIVE INGREDIENTS: AMMONIO METHACRYLATE COPOLYMER (TYPE A); AMMONIO METHACRYLATE COPOLYMER TYPE B; FERROSOFERRIC OXIDE; FD&C BLUE NO. 1; GELATIN; HYDROXYPROPYL CELLULOSE (1600000 WAMW); SODIUM LAURYL SULFATE; SUCROSE; STARCH, CORN; TALC; TITANIUM DIOXIDE; TRIETHYL CITRATE; FERRIC OXIDE YELLOW; POTASSIUM HYDROXIDE; PROPYLENE GLYCOL; SHELLAC

HIGHLIGHTS OF PRESCRIBING INFORMATION

Fluvoxamine Maleate Extended-Release Capsules
These highlights do not include all the information needed to use FLUVOXAMINE MALEATE EXTENDED-RELEASE CAPSULES safely and effectively. See full prescribing information for FLUVOXAMINE MALEATE EXTENDED-RELEASE CAPSULES.
Initial U.S. Approval: 2008

WARNING: SUICIDALITY AND ANTIDEPRESSANT DRUGS

WARNING: SUICIDALITY AND ANTIDEPRESSANTS

See full prescribing information for complete boxed warning.

Increased risk of suicidal thinking and behavior in children, adolescents, and young adults taking antidepressants for major depressive disorder and other psychiatric disorders (5.1).

1 INDICATIONS AND USAGE

Fluvoxamine maleate extended-release capsules are a selective serotonin reuptake inhibitor (SSRI) indicated for the treatment of obsessive compulsive disorder (OCD) (1). Efficacy was demonstrated in:

- One 12-week study with fluvoxamine maleate extended-release capsules in adults (14.1).
- Two 10-week studies with immediate-release (IR) fluvoxamine tablets in adults and one 10-week study with IR fluvoxamine tablets in children and adolescents (14.1, 14.3).
- One maintenance study with IR fluvoxamine tablets (14.2).

2 DOSAGE AND ADMINISTRATION

- Adults: Recommended starting dose is 100 mg at bedtime, with weekly increases of 50 mg as tolerated to maximum effect, not to exceed 300 mg/day (2.1).
- Pediatric patients naïve to fluvoxamine maleate: The lowest available dose of fluvoxamine maleate extended-release capsules may not be appropriate (2.2).
- Hepatically impaired: Decreased clearance may require modified dose and titration (2.3).
- Extended treatment: Adjust dose to maintain lowest effective dose; reassess patients periodically (2.4).
- Discontinuation: Gradual dose reduction is recommended (2.7, see Warnings and Precautions [5.10]).

3 DOSAGE FORMS AND STRENGTHS

- Extended-Release Capsules: 100 mg and 150 mg (3)

4 CONTRAINDICATIONS

- Coadministration of thioridazine, tizanidine, pimozide, alosetron, or ramelteon (4).
- Serotonin Syndrome and MAOIs: Do not use MAOIs intended to treat psychiatric disorders with fluvoxamine maleate extended-release capsules or within 14 days of stopping treatment with fluvoxamine maleate extended-release capsules. Do not use fluvoxamine maleate extended-release capsules within 14 days of stopping an MAOI intended to treat psychiatric disorders. In addition, do not start fluvoxamine maleate extended-release capsules in a patient who is being treated with linezolid or intravenous methylene blue (4.1).

5 WARNINGS AND PRECAUTIONS

- Clinical Worsening/Suicide Risk:Monitor for clinical worsening of suicidal thoughts/behaviors especially during the initial months of therapy and at times of dose changes (5.1).
- Bipolar Disorder:Screen for bipolar disorder (5.1).
- Serotonin Syndrome: Serotonin syndrome has been reported with SSRIs and SNRIs, including fluvoxamine maleate extended-release capsules, both when taken alone, but especially when coadministered with other serotonergic agents. If such symptoms occur, discontinue fluvoxamine maleate extended-release capsules and serotonergic agents and initiate supportive treatment. If concomitant use of fluvoxamine maleate extended-release capsules with other serotonergic drugs is clinically warranted, patients should be made aware of a potential increased risk for serotonin syndrome, particularly during treatment initiation and dose increases (5.2).
- Angle Closure Glaucoma:Angle closure glaucoma has occurred in patients with untreated anatomically narrow angles treated with antidepressants (5.3) .
- Other Potentially Important Drug Interactions: Benzodiazepines:Use with caution. Coadministration with diazepam is generally not advisable (5.9). Clozapine:Clozapine levels may be increased and produce orthostatic hypotension or seizures (5.9). Methadone:Coadministration may produce opioid intoxication. Discontinuation of fluvoxamine may produce opioid withdrawal (5.9). Mexiletine:Monitor serum mexiletine levels (5.9). Theophylline:Clearance decreased; reduce theophylline dose by one-third (5.9). Warfarin:Plasma concentrations increased and prothrombin times prolonged; monitor prothrombin time and adjust warfarin dose accordingly (5.9).
- Discontinuation:Symptoms associated with discontinuation have been reported (5.10). In the absence of an emergency, abrupt discontinuation not recommended (2.7, 5.2).
- Abnormal Bleeding:May increase bleeding risk, especially when used with NSAIDs, aspirin, warfarin, or other drugs that affect coagulation (5.11).
- Activation of Mania/Hypomaniahas occurred (5.12).
- Seizures:Avoid administering fluvoxamine in patients with unstable epilepsy; monitor patients with controlled epilepsy; discontinue treatment if seizures occur or frequency increases (5.13).
- Hyponatremia:May occur with SSRIs and SNRIs, including fluvoxamine maleate extended-release capsules. The elderly may be at increased risk. Consider discontinuing in patients with symptomatic hyponatremia (5.14).
- Concomitant Illness:Use caution in patients with diseases or conditions that affect hemodynamic responses or metabolism. Patients with impaired liver function may require a lower starting dose and slower titration (5.15).
- Sexual Dysfunction:Fluvoxamine may cause symptoms of sexual dysfunction (5.17).

6 ADVERSE REACTIONS

Most common reactions in controlled trials with OCD patients and patients from another studied population (incidence greater than or equal to 5% and at least twice that for placebo) were abnormal ejaculation, anorexia, anorgasmia, asthenia, diarrhea, nausea, somnolence, sweatingand tremor(6.2). The following additional reactions occurred: anxiety, decreased libido, myalgia, pharyngitis, and vomitingin the OCD population; and dyspepsia, dizziness, insomnia,and yawningin another studied population.

To report SUSPECTED ADVERSE REACTIONS, contact AvKARE at 1-855-361-3993; email drugsafety@avkare.com or FDA at 1-800-FDA-1088 or www.fda.gov/medwatch.

7 DRUG INTERACTIONS

Drug Interactions (not described in Contraindications or Warnings and Precautions) include the following:

Drugs Inhibiting or Metabolized by Cytochrome P450:Fluvoxamine inhibits several cytochrome P450 isoenzymes (CYP1A2, CYP2C9, CYP3A4, and CYP2C19) (7.1). Carbamazepine:Elevated carbamazepine levels and symptoms of toxicity with coadministration (7.2). Sumatriptan:Rare postmarketing reports of weakness, hyperreflexia, and incoordination following use of an SSRI and sumatriptan. Monitor appropriately if concomitant treatment is clinically warranted (7.2). Tacrine:Coadministration increased tacrine Cmaxand AUC five- and eight-fold and caused nausea, vomiting, sweating, and diarrhea (7.2). Tricyclic Antidepressants (TCAs):Coadministration significantly increased plasma TCA levels. Use caution; monitor plasma TCA levels; reduce TCA dose if indicated (7.2). Tryptophan:Severe vomiting with coadministration (7.2). Diltiazem:Bradycardia with coadministration (7.3). Propranolol or Metoprolol:Reduce dose if coadministered with fluvoxamine and titrate more cautiously (7.3).

8 USE IN SPECIFIC POPULATIONS

Specific populations not discussed in Dosage and Administrationor Warnings and Precautionsinclude:

- Pregnancy: Consider both potential risks and benefits when treating a pregnant woman. Infants exposed to SSRIs in pregnancy have developed various complications and may be at risk for persistent pulmonary hypertension of the newborn (PPHN) (2.7, 8.1).
- Nursing mothers: Fluvoxamine is secreted in human breast milk (8.3).
- Geriatric: Use of a lower starting dose may be warranted. Titrate slowly during initiation of therapy (2.3, 8.5).
- Smokers: Smokers had a 25% increase in fluvoxamine metabolism (7.4).

FULL PRESCRIBING INFORMATION

WARNING: SUICIDALITY AND ANTIDEPRESSANT DRUGS

Antidepressants increased the risk compared to placebo of suicidal thinking and behavior (suicidality) in children, adolescents, and young adults in short-term studies of major depressive disorder (MDD) and other psychiatric disorders. Anyone considering the use of fluvoxamine maleate extended-release capsules or any other antidepressant in a child, adolescent, or young adult must balance this risk with the clinical need. Short-term studies did not show an increase in the risk of suicidality with antidepressants compared to placebo in adults beyond age 24; there was a reduction in risk with antidepressants compared to placebo in adults aged 65 and older. Depression and certain other psychiatric disorders are themselves associated with increases in the risk of suicide. Patients of all ages who are started on antidepressant therapy should be monitored appropriately and observed closely for clinical worsening, suicidality, or unusual changes in behavior. Families and caregivers should be advised of the need for close observation and communication with the prescriber. (See Warnings and Precautions-Clinical Worsening and Suicide Risk [5.1]and Use in Specific Populations-Pediatric Use [8.4].)

1 INDICATIONS AND USAGE

1.1 Obsessive Compulsive Disorder

Fluvoxamine maleate extended-release capsules are indicated for the treatment of obsessive compulsive disorder (OCD), as defined in the DSM-IV. Obsessive compulsive disorder is characterized by recurrent and persistent ideas, thoughts, impulses, or images (obsessions) that are ego-dystonic and/or repetitive, purposeful, and intentional behaviors (compulsions) that are recognized by the person as excessive or unreasonable. The obsessions or compulsions cause marked distress, are time-consuming, or significantly interfere with social or occupational functioning.

The efficacy of fluvoxamine maleate extended-release capsules was demonstrated in one 12-week trial in adults with fluvoxamine maleate extended-release capsules as well as in two 10-week trials in adults and in one 10-week trial in children and adolescents (ages 8 to 17 years) with immediate-release fluvoxamine tablets in outpatients with the diagnosis of OCD as defined in DSM-IV or DSM-III-R (see Clinical Studies [14.1, 14.3]) .

The efficacy of fluvoxamine for long-term use was established in one maintenance study in adults with immediate-release fluvoxamine tablets (see Clinical Studies [14.2]) . The health care provider who elects to prescribe fluvoxamine maleate extended-release capsules for extended periods should periodically re-evaluate the long-term usefulness of the drug for the individual patient (see Dosage and Administration [2.4]) .

2 DOSAGE AND ADMINISTRATION

2.1 OCD (Obsessive Compulsive Disorder)

The recommended starting dose is 100 mg at bedtime, with weekly increases of 50 mg as tolerated to maximum therapeutic benefit, not to exceed 300 mg per day.

Capsules should not be crushed or chewed.

2.2 Pediatric Patients Naïve to Fluvoxamine Maleate

Physicians should consider that the lowest available dose of fluvoxamine maleate extended-release capsules may not be appropriate for pediatric patients naïve to fluvoxamine maleate.

2.3 Dosage for Elderly or Hepatically Impaired Patients

Elderly patients and those with hepatic impairment have been observed to have a decreased clearance of fluvoxamine maleate. Consequently, it may be appropriate to titrate slowly following the initial dose of 100 mg in these patient groups.

2.4 Maintenance/Continuation of Extended Treatment

Although the efficacy of fluvoxamine maleate extended-release capsules beyond 12 weeks of dosing has not been documented in controlled trials, OCD is a chronic condition, and it is reasonable to consider continuation for a responding patient. The benefit of maintaining patients with OCD on immediate-release fluvoxamine maleate tablets after achieving a response for an average duration of about 4 weeks in a 10-week single-blind phase during which patients were titrated to effect was demonstrated in a controlled trial (see Clinical Studies [14.2]) . Dosage adjustments should be made to maintain the patient on the lowest effective dosage, and patients should be periodically reassessed to determine the need for continued treatment.

2.5 Switching a Patient To or From a Monoamine Oxidase Inhibitor (MAOI) Intended to Treat Psychiatric Disorders

At least 14 days should elapse between discontinuation of an MAOI intended to treat psychiatric disorders and initiation of therapy with fluvoxamine maleate extended-release capsules. Conversely, at least 14 days should be allowed after stopping fluvoxamine maleate extended-release capsules before starting an MAOI intended to treat psychiatric disorders (see Contraindications [4.1]) .

2.6 Use of Fluvoxamine Maleate Extended-Release Capsules with Other MAOIs such as Linezolid or Methylene Blue

Do not start fluvoxamine maleate extended-release capsules in a patient who is being treated with linezolid or intravenous methylene blue because there is an increased risk of serotonin syndrome. In a patient who requires more urgent treatment of a psychiatric condition, other interventions, including hospitalization, should be considered (see Contraindications [4.1]).

In some cases, a patient already receiving fluvoxamine maleate extended-release capsules therapy may require urgent treatment with linezolid or intravenous methylene blue. If acceptable alternatives to linezolid or intravenous methylene blue treatment are not available and the potential benefits of linezolid or intravenous methylene blue treatment are judged to outweigh the risks of serotonin syndrome in a particular patient, fluvoxamine maleate extended-release capsules should be stopped promptly, and linezolid or intravenous methylene blue can be administered. The patient should be monitored for symptoms of serotonin syndrome for two weeks or until 24 hours after the last dose of linezolid or intravenous methylene blue, whichever comes first. Therapy with fluvoxamine maleate extended-release capsules may be resumed 24 hours after the last dose of linezolid or intravenous methylene blue (see Warnings and Precautions [5.2]) .

The risk of administering methylene blue by non-intravenous routes (such as oral tablets or by local injection) or in intravenous doses much lower than 1 mg/kg with fluvoxamine maleate extended-release capsules is unclear. The clinician should, nevertheless, be aware of the possibility of emergent symptoms of serotonin syndrome with such use (see Warnings and Precautions [5.2]) .

2.7 Discontinuation of Treatment with Fluvoxamine Maleate Extended-Release Capsules

Symptoms associated with discontinuation of other SSRIs or SNRIs have been reported (see Warnings and Precautions [5.10]) . Patients should be monitored for these symptoms when discontinuing treatment. A gradual reduction in the dose rather than abrupt cessation is recommended whenever possible. If intolerable symptoms occur following a decrease in the dose or upon discontinuation of treatment, then resuming the previously prescribed dose may be considered. Subsequently, the health care provider may continue decreasing the dose but at a more gradual rate.

3 DOSAGE FORMS AND STRENGTHS

Fluvoxamine maleate extended-release capsules are available as:

100 mg – Each #2 capsule with olive opaque cap and gray opaque body, imprinted with and 2848 on both cap and body in black ink contains 100 mg of fluvoxamine maleate, USP.

150 mg – Each #1 capsule with olive opaque cap and white opaque body, imprinted with and 2849 on both cap and body in black ink contains 150 mg of fluvoxamine maleate, USP.

4 CONTRAINDICATIONS

Coadministration of thioridazine, tizanidine, pimozide, alosetron, or ramelteon with fluvoxamine maleate extended-release capsules is contraindicated (see Warnings and Precautions [5.4 to 5.8]) .

4.1 Monoamine Oxidase Inhibitors (MAOIs)

The use of MAOIs intended to treat psychiatric disorders with fluvoxamine maleate extended-release capsules or within 14 days of stopping treatment with fluvoxamine maleate extended-release capsules is contraindicated because of an increased risk of serotonin syndrome. The use of fluvoxamine maleate extended-release capsules within 14 days of stopping an MAOI intended to treat psychiatric disorders is also contraindicated (see Dosage and Administration [2.5] and Warnings and Precautions [5.2]) .

Starting fluvoxamine maleate extended-release capsules in a patient who is being treated with MAOIs such as linezolid or intravenous methylene blue is also contraindicated because of an increased risk of serotonin syndrome (see Dosage and Administration [2.6]and Warnings and Precautions [5.2]).

5 WARNINGS AND PRECAUTIONS

5.1 Clinical Worsening and Suicide Risk

Patients with major depressive disorder (MDD), both adult and pediatric, may experience worsening of their depression and/or the emergence of suicidal ideation and behavior (suicidality) or unusual changes in behavior, whether or not they are taking antidepressant medications, and this risk may persist until significant remission occurs. Suicide is a known risk of depression and certain other psychiatric disorders, and these disorders themselves are the strongest predictors of suicide. There has been a long-standing concern, however, that antidepressants may have a role in inducing worsening of depression and the emergence of suicidality in certain patients during the early phases of treatment. The pooled analyses of short-term placebo-controlled trials of antidepressant drugs (SSRIs and others) showed that these drugs increase the risk of suicidal thinking and behavior (suicidality) in children, adolescents, and young adults (ages 18 to 24) with major depressive disorder (MDD) and other psychiatric disorders. Short-term studies did not show an increase in the risk of suicidality with antidepressants compared to placebo in adults beyond age 24; there was a reduction with antidepressants compared to placebo in adults age 65 and older.

The pooled analyses of placebo-controlled trials in children and adolescents with MDD, obsessive compulsive disorder (OCD), or other psychiatric disorders included a total of 24 short-term trials of 9 antidepressant drugs in over 4400 patients. The pooled analyses of placebo-controlled trials in adults with MDD or other psychiatric disorders included a total of 295 short-term trials (median duration of 2 months) of 11 antidepressant drugs in over 77,000 patients. There was considerable variation in risk of suicidality among drugs, but a tendency toward an increase in the younger patients for almost all drugs studied. There were differences in absolute risk of suicidality across the different indications, with the highest incidence in MDD. The risk differences (drug vs placebo), however, were relatively stable within age strata and across indications. These risk differences (drug-placebo difference in the number of cases of suicidality per 1,000 patients treated) are provided in Table 1.

Table 1: Drug-Placebo Differences in Number of Cases of Suicidality Per 1,000 Patients Treated
Age Range | Drug-Related Increases
<18 | 14 additional cases
18 to 24 | 5 additional cases
Age Range | Drug-Related Decreases
25 to 64 | 1 fewer case
≥ 65 | 6 fewer cases

No suicides occurred in any of the pediatric trials. There were suicides in the adult trials, but the number was not sufficient to reach any conclusion about the drug effect on suicide.

It is unknown whether the suicidality risk extends to longer-term use, i.e., beyond several months. However, there is substantial evidence from placebo-controlled maintenance trials in adults with depression that the use of antidepressants can delay the recurrence of depression.

All patients being treated with antidepressants for any indication should be monitored appropriately and observed closely for clinical worsening, suicidality, and unusual changes in behavior, especially during the initial few months of a course of drug therapy, or at times of dose changes, either increases or decreases.

The following symptoms, anxiety, agitation, panic attacks, insomnia, irritability, hostility, aggressiveness, impulsivity, akathisia (psychomotor restlessness), hypomania, and mania, have been reported in adult and pediatric patients being treated with antidepressants for major depressive disorder as well as for other indications, both psychiatric and nonpsychiatric. Although a causal link between the emergence of such symptoms and either the worsening of depression and/or the emergence of suicidal impulses has not been established, there is concern that such symptoms may represent precursors to emerging suicidality.

Consideration should be given to changing the therapeutic regimen, including possibly discontinuing the medication, in patients whose depression is persistently worse, or who are experiencing emergent suicidality or symptoms that might be precursors to worsening depression or suicidality, especially if these symptoms are severe, abrupt in onset, or were not part of the patient’s presenting symptoms.

If the decision has been made to discontinue treatment, medication should be tapered, as rapidly as is feasible, but with recognition that abrupt discontinuation can be associated with certain symptoms (see Dosage and Administration–Discontinuation of Treatment with Fluvoxamine Maleate Extended-Release Capsules [2.7], for a description of the risks of discontinuation of fluvoxamine maleate extended-release capsules).

Families and caregivers of patients being treated with antidepressants for major depressive disorder or other indications, both psychiatric and nonpsychiatric, should be alerted about the need to monitor patients for the emergence of agitation, irritability, unusual changes in behavior, and the other symptoms described above, as well as the emergence of suicidality, and to report such symptoms immediately to health care providers. Such monitoring should include daily observation by families and caregivers.Prescriptions for fluvoxamine maleate extended-release capsules should be written for the smallest quantity of capsules consistent with good patient management, in order to reduce the risk of overdose.

Screening Patients for Bipolar Disorder:A major depressive episode may be the initial presentation of bipolar disorder. It is generally believed (though not established in controlled trials) that treating such an episode with an antidepressant alone may increase the likelihood of precipitation of a mixed/manic episode in patients at risk for bipolar disorder. Whether any of the symptoms described above represent such a conversion is unknown. However, prior to initiating treatment with an antidepressant, patients with depressive symptoms should be adequately screened to determine if they are at risk for bipolar disorder; such screening should include a detailed psychiatric history, including a family history of suicide, bipolar disorder, and depression. It should be noted that fluvoxamine maleate extended-release capsules are not approved for use in treating bipolar depression.

5.2 Serotonin Syndrome

The development of a potentially life-threatening serotonin syndrome has been reported with SNRIs and SSRIs, including fluvoxamine maleate extended-release capsules, alone but particularly with concomitant use of serotonergic drugs (including triptans, tricyclic antidepressants, fentanyl, meperidine, methadone, lithium, tramadol, tryptophan, buspirone, amphetamines, and St. John’s Wort), and with drugs that impair metabolism of serotonin (in particular, MAOIs, both those intended to treat psychiatric disorders and also others, such as linezolid and intravenous methylene blue).

Serotonin syndrome symptoms may include mental status changes (e.g., agitation, hallucinations, delirium, and coma), autonomic instability (e.g., tachycardia, labile blood pressure, dizziness, diaphoresis, flushing, hyperthermia), neuromuscular symptoms (e.g., tremor, rigidity, myoclonus, hyperreflexia, incoordination), seizures, and/or gastrointestinal symptoms (e.g., nausea, vomiting, diarrhea). Patients should be monitored for the emergence of serotonin syndrome.

The concomitant use of fluvoxamine maleate extended-release capsules with MAOIs intended to treat psychiatric disorders is contraindicated. Fluvoxamine maleate extended-release capsules should also not be started in a patient who is being treated with MAOIs such as linezolid or intravenous methylene blue. All reports with methylene blue that provided information on the route of administration involved intravenous administration in the dose range of 1 mg/kg to 8 mg/kg. No reports involved the administration of methylene blue by other routes (such as oral tablets or local tissue injection) or at lower doses. There may be circumstances when it is necessary to initiate treatment with an MAOI such as linezolid or intravenous methylene blue in a patient taking fluvoxamine maleate extended-release capsules. Fluvoxamine maleate extended-release capsules should be discontinued before initiating treatment with the MAOI (see Contraindications [4.1]and Dosage and Administration [2.5, 2.6]) .

If concomitant use of fluvoxamine maleate extended-release capsules with other serotonergic drugs, including triptans, tricyclic antidepressants, fentanyl, lithium, tramadol, tryptophan, buspirone, amphetamines, and St. John's Wort, is clinically warranted, patients should be made aware of a potential increased risk for serotonin syndrome, particularly during treatment initiation and dose increases.

Treatment with fluvoxamine maleate extended-release capsules and any concomitant serotonergic agents should be discontinued immediately if the above events occur, and supportive symptomatic treatment should be initiated.

5.3 Angle Closure Glaucoma

Angle Closure Glaucoma: The pupillary dilation that occurs following use of many antidepressant drugs including fluvoxamine maleate extended-release capsules may trigger an angle closure attack in a patient with anatomically narrow angles who does not have a patent iridectomy.

5.4 Potential Thioridazine Interaction

The effect of fluvoxamine (25 mg immediate-release tablets given twice daily for one week) on thioridazine steady-state concentrations was evaluated in 10 male inpatients with schizophrenia. Concentrations of thioridazine and its two active metabolites, mesoridazine and sulforidazine, increased 3-fold following coadministration of fluvoxamine.

Thioridazine administration produces a dose-related prolongation of the QTc interval, which is associated with serious ventricular arrhythmias, such as torsades de pointes-type arrhythmias, and sudden death. It is likely that this experience underestimates the degree of risk that might occur with higher doses of thioridazine. Moreover, the effect of fluvoxamine may be even more pronounced when it is administered at higher doses.

Therefore, fluvoxamine maleate extended-release capsules should not be coadministered with thioridazine (see Contraindications [4]) .

5.5 Potential Tizanidine Interaction

Fluvoxamine is a potent inhibitor of CYP1A2, and tizanidine is a CYP1A2 substrate. The effect of immediate-release fluvoxamine maleate tablets (100 mg daily for four days) on the pharmacokinetics and pharmacodynamics of a single dose of tizanidine has been studied in 10 healthy male subjects. Tizanidine Cmaxwas increased approximately 12-fold (range 5-fold to 32-fold), elimination half-life was increased by almost 3-fold, and AUC increased 33-fold (range 14-fold to 103-fold). The mean maximal effect on blood pressure was a 35 mm Hg decrease in systolic blood pressure, a 20 mm Hg decrease in diastolic blood pressure, and a 4 beat/min decrease in heart rate. Drowsiness was significantly increased, and performance on the psychomotor task was significantly impaired. Fluvoxamine maleate extended-release capsules and tizanidine should not be used together (see Contraindications [4]) .

5.6 Potential Pimozide Interaction

Pimozide is metabolized by the CYP3A4 isozyme and it has been demonstrated that ketoconazole, a potent inhibitor of CYP3A4, blocks the metabolism of this drug, resulting in increased plasma concentrations of parent drug. An increased plasma concentration of pimozide causes QT prolongation and has been associated with torsades de pointes-type ventricular tachycardia, sometimes fatal. As noted below, a substantial pharmacokinetic interaction has been observed for fluvoxamine in combination with alprazolam, a drug that is known to be metabolized by the CYP3A4 isozyme. Although it has not been definitively demonstrated that fluvoxamine is a potent CYP3A4 inhibitor, it is likely to be, given the substantial interaction of fluvoxamine with alprazolam. Consequently, it is recommended that fluvoxamine not be used in combination with pimozide (see Contraindications [4]) .

5.7 Potential Alosetron Interaction

In a pharmacokinetic study, 40 healthy female subjects received fluvoxamine in escalating doses from 50 to 200 mg/day for 16 days with coadministration of alosetron 1 mg on the last day. Fluvoxamine increased mean alosetron plasma concentrations (AUC) approximately 6-fold and prolonged the half-life by approximately 3-fold. Consequently, it is recommended that fluvoxamine maleate extended-release capsules not be used in combination with alosetron (see Contraindications [4] and Lotronex®(alosetron) package insert).

5.8 Potential Ramelteon Interaction

When immediate-release fluvoxamine maleate tablets 100 mg twice daily were administered for 3 days prior to single-dose coadministration of ramelteon 16 mg and immediate-release fluvoxamine maleate tablets, the AUC for ramelteon increased approximately 190-fold and the Cmaxincreased approximately 70-fold compared to ramelteon administered alone. Ramelteon should not be used in combination with fluvoxamine maleate extended-release capsules (see Contraindications [ 4]) .

5.9 Other Potentially Important Drug Interactions

Benzodiazepines:Benzodiazepines metabolized by hepatic oxidation (e.g., alprazolam, midazolam, triazolam, etc.) should be used with caution because the clearance of these drugs is likely to be reduced by fluvoxamine. The clearance of benzodiazepines metabolized by glucuronidation (e.g., lorazepam, oxazepam, temazepam) is unlikely to be affected by fluvoxamine.

Alprazolam- When immediate-release fluvoxamine maleate tablets (100 mg given once daily) and alprazolam (1 mg given 4 times per day) were coadministered to steady state, plasma concentrations and other pharmacokinetic parameters (AUC, Cmax, T1/2) of alprazolam were approximately twice those observed when alprazolam was administered alone; oral clearance was reduced by about 50%. The elevated plasma alprazolam concentrations resulted in decreased psychomotor performance and memory. This interaction, which has not been investigated using higher doses of fluvoxamine, may be more pronounced if a 300 mg daily dose is coadministered, particularly since fluvoxamine exhibits non-linear pharmacokinetics over the dosage range 100 to 300 mg. If alprazolam is coadministered with fluvoxamine maleate extended-release capsules, the initial alprazolam dosage should be at least halved and titration to the lowest effective dose is recommended. No dosage adjustment is required for fluvoxamine maleate extended-release capsules.

Diazepam- The coadministration of fluvoxamine maleate extended-release capsules and diazepam is generally not advisable. Because fluvoxamine reduces the clearance of both diazepam and its active metabolite, N-desmethyldiazepam, there is a strong likelihood of substantial accumulation of both species during chronic coadministration.

Evidence supporting the conclusion that it is inadvisable to coadminister fluvoxamine and diazepam is derived from a study in which healthy volunteers taking 150 mg/day of immediate-release fluvoxamine maleate tablets were administered a single oral dose of 10 mg of diazepam. In these subjects (N=8), the clearance of diazepam was reduced by 65% and that of N-desmethyldiazepam to a level that was too low to measure over the course of the 2-week-long study.

It is likely that this experience significantly underestimates the degree of accumulation that might occur with repeated diazepam administration. Moreover, as noted with alprazolam, the effect of fluvoxamine may even be more pronounced when it is administered at higher doses.

Accordingly, diazepam and fluvoxamine should not ordinarily be coadministered.

Clozapine:Elevated serum levels of clozapine have been reported in patients taking immediate-release fluvoxamine maleate tablets and clozapine. Since clozapine-related seizures and orthostatic hypotension appear to be dose related, the risk of these adverse reactions may be higher when fluvoxamine and clozapine are coadministered. Patients should be closely monitored when fluvoxamine maleate extended-release capsules and clozapine are used concurrently.

Methadone:Significantly increased methadone (plasma level:dose) ratios have been reported when immediate-release fluvoxamine maleate tablets were administered to patients receiving maintenance methadone treatment, with symptoms of opioid intoxication in one patient. Opioid withdrawal symptoms were reported following fluvoxamine maleate discontinuation in another patient.

Mexiletine:The effect of steady-state fluvoxamine (50 mg given twice daily for 7 days) on the single dose pharmacokinetics of mexiletine (200 mg) was evaluated in 6 healthy Japanese males. The clearance of mexiletine was reduced by 38% following coadministration with fluvoxamine compared to mexiletine alone. If fluvoxamine and mexiletine are coadministered, serum mexiletine levels should be monitored.

Theophylline:The effect of steady-state immediate-release fluvoxamine maleate tablets (50 mg tablets given twice daily) on the pharmacokinetics of a single dose of theophylline (375 mg as 442 mg aminophylline) was evaluated in 12 healthy non-smoking, male volunteers. The clearance of theophylline was decreased approximately 3-fold. Therefore, if theophylline is coadministered with fluvoxamine maleate, its dose should be reduced to one-third of the usual daily maintenance dose and plasma concentrations of theophylline should be monitored. No dosage adjustment is required for fluvoxamine maleate extended-release capsules.

Warfarin and Other Drugs that Interfere with Hemostasis (NSAIDs, Aspirin, etc.):Serotonin release by platelets plays an important role in hemostasis. Epidemiological studies of the case-control and cohort design have demonstrated an association between use of psychotropic drugs that interfere with serotonin reuptake and the occurrence of upper gastrointestinal bleeding. These studies have also shown that concurrent use of an NSAID or aspirin may potentiate this risk of bleeding. Thus, patients should be cautioned about the use of such drugs concurrently with fluvoxamine (see Warnings and Precautions-Abnormal Bleeding [ 5.11]) .

Warfarin- When immediate-release fluvoxamine maleate tablets (50 mg given three times daily) were administered concomitantly with warfarin for two weeks, warfarin plasma concentrations increased by 98% and prothrombin times were prolonged. Thus patients receiving oral anticoagulants and fluvoxamine maleate extended-release capsules should have their prothrombin time monitored and their anticoagulant dose adjusted accordingly. No dosage adjustment is required for fluvoxamine maleate extended-release capsules.

5.10 Discontinuation of Treatment with Fluvoxamine Maleate Extended-Release Capsules

During marketing of immediate-release fluvoxamine maleate tablets and other SSRIs and SNRIs (serotonin and norepinephrine reuptake inhibitors), there have been spontaneous reports of adverse reactions occurring upon discontinuation of these drugs, particularly when abrupt, including the following: dysphoric mood, irritability, agitation, dizziness, sensory disturbances (e.g., paresthesias, such as electric shock sensations), anxiety, confusion, headache, lethargy, emotional lability, insomnia, and hypomania. While these reactions are generally self-limiting, there have been reports of serious discontinuation symptoms.

Patients should be monitored for these symptoms when discontinuing treatment with fluvoxamine maleate extended-release capsules. A gradual reduction in the dose rather than abrupt cessation is recommended whenever possible. If intolerable symptoms occur following a decrease in the dose or upon discontinuation of treatment, then resuming the previously prescribed dose may be considered. Subsequently, the health care provider may continue decreasing the dose but at a more gradual rate (see Dosage and Administration [2.7]) .

5.11 Abnormal Bleeding

SSRIs and SNRIs, including fluvoxamine maleate extended-release capsules, may increase the risk of bleeding events. Concomitant use of aspirin, nonsteroidal anti-inflammatory drugs, warfarin, and other anticoagulants may add to this risk. Case reports and epidemiological studies (case-control and cohort design) have demonstrated an association between use of drugs that interfere with serotonin reuptake and the occurrence of gastrointestinal bleeding. Based on data from the published observational studies, exposure to SSRIs, particularly in the month before delivery, has been associated with a less than 2-fold increase in the risk of postpartum hemorrhage [see Use in Specific Populations (8.1)] . Bleeding events related to SSRIs and SNRIs use have ranged from ecchymoses, hematomas, epistaxis, and petechiae to life-threatening hemorrhages.

Patients should be cautioned about the increased risk of bleeding associated with the concomitant use of fluvoxamine maleate extended-release capsules and NSAIDs, aspirin, or other drugs that affect coagulation (see Warnings and Precautions [5.9]) .

5.12 Activation of Mania/Hypomania

During premarketing studies of immediate-release fluvoxamine maleate tablets involving primarily depressed patients, hypomania or mania occurred in approximately 1% of patients treated with fluvoxamine. In a 10-week pediatric OCD study, 2 out of 57 patients (4%) treated with fluvoxamine experienced manic reactions, compared to none of 63 placebo patients. Activation of mania/hypomania has also been reported in a small proportion of patients with major affective disorder who were treated with other marketed antidepressants. As with all antidepressants, fluvoxamine maleate extended-release capsules should be used cautiously in patients with a history of mania.

5.13 Seizures

During premarketing studies with immediate-release fluvoxamine maleate tablets, seizures were reported in 0.2% of fluvoxamine-treated patients. Caution is recommended when the drug is administered to patients with a history of convulsive disorders. Fluvoxamine should be avoided in patients with unstable epilepsy, and patients with controlled epilepsy should be carefully monitored. Treatment with fluvoxamine should be discontinued if seizures occur or if seizure frequency increases.

5.14 Hyponatremia

Hyponatremia may occur as a result of treatment with SSRIs and SNRIs, including fluvoxamine maleate extended-release capsules. In many cases, this hyponatremia appears to be the result of the syndrome of inappropriate antidiuretic hormone secretion (SIADH). Cases with serum sodium lower than 110 mmol/L have been reported. Elderly patients may be at greater risk of developing hyponatremia with SSRIs and SNRIs (see Use in Specific Populations, Geriatric Use [8.5]) . Also, patients taking diuretics or who are otherwise volume depleted may be at greater risk. Discontinuation of fluvoxamine maleate extended-release capsules should be considered in patients with symptomatic hyponatremia and appropriate medical intervention should be instituted.

Signs and symptoms of hyponatremia include headache, difficulty concentrating, memory impairment, confusion, weakness, and unsteadiness, which may lead to falls. Signs and symptoms associated with more severe and/or acute cases have included hallucination, syncope, seizure, coma, respiratory arrest, and death.

5.15 Use in Patients with Concomitant Illness

Closely monitored clinical experience with fluvoxamine maleate extended-release capsules in patients with concomitant systemic illness is limited. Caution is advised in administering fluvoxamine maleate extended-release capsules to patients with diseases or conditions that could affect hemodynamic responses or metabolism.

Fluvoxamine maleate extended-release capsules or immediate-release fluvoxamine maleate tablets have not been evaluated or used to any appreciable extent in patients with a recent history of myocardial infarction or unstable heart disease. Patients with these diagnoses were systematically excluded from many clinical studies during premarketing testing of these products. Evaluation of the electrocardiograms for patients with depression or OCD who participated in premarketing studies revealed no differences between fluvoxamine and placebo in the emergence of clinically important ECG changes.

Patients with Hepatic Impairment- In patients with liver dysfunction, following administration of immediate-release fluvoxamine maleate tablets, fluvoxamine clearance was decreased by approximately 30%. Patients with liver dysfunction should begin with a low dose of fluvoxamine maleate extended-release capsules and increase it slowly with careful monitoring.

5.16 Laboratory Tests

There are no specific laboratory tests recommended.

5.17 Sexual Dysfunction

Use of SSRIs, including fluvoxamine, may cause symptoms of sexual dysfunction [see Adverse Reactions (6.1)] . In male patients, SSRI use may result in ejaculatory delay or failure, decreased libido, and erectile dysfunction. In female patients, SSRI use may result in decreased libido and delayed or absent orgasm.

It is important for prescribers to inquire about sexual function prior to initiation of fluvoxamine and to inquire specifically about changes in sexual function during treatment, because sexual function may not be spontaneously reported. When evaluating changes in sexual function, obtaining a detailed history (including timing of symptom onset) is important because sexual symptoms may have other causes, including the underlying psychiatric disorder. Discuss potential management strategies to support patients in making informed decisions about treatment.

6 ADVERSE REACTIONS

Because clinical trials are conducted under widely varying conditions, adverse reaction rates observed in the clinical trials of a drug cannot be directly compared to rates in the clinical trials of another drug and may not reflect the rates observed in clinical practice.

6.1 Clinical Trial Data Sources

Fluvoxamine maleate extended-release capsules were studied in one 12-week controlled trial in patients with OCD (N = 124; mean exposure 66.6 days) and in two 12-week controlled trials for another condition (N = 279; mean exposure 59.2 days). Patients in these trials were initiated on 100 mg/day and were titrated in 50 mg increments over the first 6 weeks to within a range of 100 mg to 300 mg/day. The reactions listed in Table 2 show reactions from the two populations separately. Table 3 shows reactions from the three controlled studies combined.

6.2 Adverse Reactions Observed in Controlled Trials

Adverse Reactions Associated with Discontinuation of Treatment:Of the 124 patients with OCD and 279 patients in other studies treated with fluvoxamine maleate extended-release capsules in controlled clinical trials, 19% and 26% discontinued treatment due to an adverse reaction. The most common reactions (greater than or equal to 1%) associated with discontinuation and considered to be drug related (i.e., those reactions associated with dropout at a rate at least twice that of placebo) were anorexia(including, but not limited to, loss of appetite and decreased appetite) (1%), anxiety (3%), asthenia (3%), diarrhea (2%), dizziness (4%), headache (2%), insomnia (5%), nausea (7%), nervousness (1%), somnolence (5%), and thinking abnormal (1%).

Commonly Observed Adverse Reactions:Fluvoxamine maleate extended-release capsules have been studied in one controlled trial in patients with OCD (N = 124) and two controlled trials for another condition (N = 279). In general, adverse reaction rates were similar in the two data sets as well as in a study of pediatric patients with OCD treated with immediate-release fluvoxamine maleate tablets. The most commonly observed treatment-emergent adverse reactions associated with the use of fluvoxamine maleate extended-release capsules and likely to be drug-related (incidence of 5% or greater and at least twice that for placebo) and derived from Table 2 were: abnormal ejaculation, anorexia, anorgasmia, asthenia, diarrhea, nausea, somnolence, sweating, and tremor. In the one controlled trial in patients with OCD, the following additional reactions occurred at an incidence of 5% or greater and at least twice that for placebo: anxiety, decreased libido, myalgia, pharyngitis, and vomiting. The following additional reactions occurred in another studied population: dyspepsia, dizziness, insomnia, and yawning. In a study evaluating immediate-release fluvoxamine maleate tablets in pediatric patients with OCD, the following additional reactions were identified using the above rule: agitation, depression, dysmenorrhea, flatulence, hyperkinesia, and rash.

Adverse Reactions Occurring at an Incidence of Greater Than or Equal To 2%:Table 2 enumerates adverse reactions that occurred in adults at a frequency of 2% or more, and were more frequent than in the placebo group, among patients treated with fluvoxamine maleate extended-release capsules in two short-term, placebo-controlled trials (12 weeks) in another population and one short-term placebo-controlled OCD trial (12 weeks) and in which patients were dosed once-a-day in a range of 100 to 300 mg/day. This table shows the percentage of patients in each group who had at least one occurrence of a reaction at some time during their treatment. Reported adverse reactions were classified using a COSTART-based Dictionary terminology.

The prescriber should be aware that these figures cannot be used to predict the incidence of side effects in the course of usual medical practice where patient characteristics and other factors may differ from those that prevailed in the clinical trials. Similarly, the cited frequencies cannot be compared with figures obtained from other clinical investigations involving different treatments, uses, and investigators. The cited figures, however, do provide the prescribing health care provider with some basis for estimating the relative contribution of drug and non-drug factors to the side-effect incidence rate in the population studied.

Table 2: Treatment-Emergent Adverse Reaction Incidence Rates by Body System in Adult OCD Patients and Another Studied Population^1
PERCENTAGE OF PATIENTS REPORTING REACTION
 | OBSESSIVE COMPULSIVE DISORDER |  | OTHER STUDIED POPULATION
BODY SYSTEM/ | FLUVOXAMINE MALEATE |  | FLUVOXAMINE MALEATE
 | EXTENDED-RELEASE | PLACEBO | EXTENDED-RELEASE | PLACEBO
ADVERSE REACTION | N = 124 | N = 124 | N = 279 | N = 276
BODY AS A WHOLE
Headache | 32 | 31 | 35 | 30
Asthenia | 26 | 8 | 24 | 10
Pain^2 | 10 | 8 | – | –
Abdominal Pain | – | – | 5 | 4
Accidental Injury | 5 | 3 | – | –
Chest Pain | – | – | 3 | 1
Viral Infection | 2 | <1 | – | –
CARDIOVASCULAR
Palpitation | – | – | 3 | 1
Vasodilatation | – | – | 2 | <1
Hypertension | 2 | <1 | – | –
DIGESTIVE SYSTEM
Nausea | 34 | 13 | 39 | 11
Diarrhea | 18 | 8 | 14 | 5
Anorexia^3 | 13 | 5 | 14 | 1
Dyspepsia | 8 | 5 | 10 | 4
Constipation | 4 | <1 | 6 | 5
Vomiting | 6 | 2 | – | –
Tooth Disorder | 2 | <1 | – | –
Liver Function Test Abnormal | – | – | 2 | <1
Gingivitis | 2 | 0 | – | –
HEMIC AND LYMPHATIC
Ecchymosis | 4 | 2 | – | –
METABOLIC AND NUTRITIONAL DISORDERS
Weight Loss | 2 | <1 | – | –
MUSCULOSKELETAL
Myalgia | 5 | 2 | – | –
NERVOUS SYSTEM
Insomnia | 35 | 20 | 32 | 13
Somnolence | 27 | 11 | 26 | 9
Dizziness | 12 | 10 | 15 | 7
Dry Mouth | 10 | 9 | 11 | 8
Nervousness | – | – | 10 | 9
Libido Decreased | 6 | 2 | 6 | 4
Male | 10 | 5 | 8 | 6
Female | 4 | 1 | 4 | 3
Anxiety | 6 | 2 | 8 | 5
Tremor | 6 | 0 | 8 | <1
Abnormal Thinking | 3 | <1 | 3 | 2
Abnormal Dreams | – | – | 3 | 2
Agitation | 2 | <1 | 3 | <1
Hypertonia | – | – | 2 | 1
Apathy | 3 | 0 | – | –
Paresthesia | – | – | 3 | 2
Neurosis | 2 | <1 | – | –
Twitching | 2 | 0 | – | –
RESPIRATORY SYSTEM
Pharyngitis | 6 | <1 | – | –
Yawn | 2 | 0 | 5 | <1
Laryngitis | 3 | 0 | – | –
Bronchitis | – | – | 2 | 1
Epistaxis | 2 | 0 | – | –
SKIN
Sweating | 7 | <1 | 6 | 2
Acne | 2 | 0 | – | –
SPECIAL SENSES
Taste Perversion | 2 | <1 | 2 | <1
Amblyopia | 2 | <1 | – | –
UROGENITAL
Abnormal Ejaculation | 10 | 0 | 11 | 2
Anorgasmia | 5 | 0 | 5 | 1
Male | 4 | 0 | 4 | 2
Female | 5 | 0 | 5 | 0
Menorrhagia | 3 | 0 | – | –
Sexual Function Abnormal | 2 | <1 | 3 | <1
Male | 4 | 3 | 2 | 1
Female | 0 | 0 | 3 | 0
Urinary Tract Infection | – | – | 2 | <1
Polyuria | 2 | <1 | – | –
^1Events for which fluvoxamine maleate incidence was equal to or less than placebo include the following for OCD patients: abdominal pain, flu syndrome, infection, palpitation, flatulence, increased appetite, weight gain, abnormal dreams, amnesia, hypertonia, nervousness, paresthesia, increased cough, dyspnea, rhinitis, and ear pain. In the other studied population the following events were seen: abdominal pain, accidental injury, back pain, flu syndrome, infection, pain, flatulence, pharyngitis, rhinitis, rash, and dysmenorrhea.
^2Term includes body aches/pains, dental pain, pain from surgery, unspecified pain, and general pain secondary to injuries (sprains, fractures).
^3Includes, but is not limited to, loss of appetite and decreased appetite.

6.3 Other Adverse Reactions in OCD Pediatric Population

In pediatric patients (N=57) treated with immediate-release fluvoxamine maleate tablets, the overall profile of adverse reactions was generally similar to that seen in adult studies, as shown in Table 2. However, the following adverse reactions, not appearing in Table 2, were reported in two or more of the pediatric patients and were more frequent with immediate-release fluvoxamine maleate tablets than with placebo: cough increase, dysmenorrhea, ecchymosis, emotional lability, epistaxis, hyperkinesia, manic reaction, rash, sinusitis, and weight decrease.

6.4 Male and Female Sexual Dysfunction with SSRIs

Although changes in sexual desire, sexual performance, and sexual satisfaction often occur as manifestations of a psychiatric disorder and with aging, they may also be a consequence of pharmacologic treatment. In particular, some evidence suggests that selective serotonin reuptake inhibitors (SSRIs) can cause such untoward sexual experiences.

Reliable estimates of the incidence and severity of untoward experiences involving sexual desire, performance, and satisfaction are difficult to obtain, however, in part because patients and health care providers may be reluctant to discuss them. Accordingly, estimates of the incidence of untoward sexual experience and performance cited in product labeling are likely to underestimate their actual incidence.

Table 3 displays the incidence of sexual side effects reported by at least 2% of patients taking fluvoxamine maleate extended-release capsules in placebo-controlled trials.

Table 3: Percentage of Patients Reporting Sexual Adverse Reactions in Placebo-Controlled Trials
 | FLUVOXAMINE MALEATE EXTENDED-RELEASE | Placebo
 | N = 403 | N = 400
Abnormal Ejaculation | 11 | 2
Anorgasmia
Male | 4 | 1
Female | 5 | 0
Impotence | 2 | 2
Libido Decreased
Male | 8 | 5
Female | 4 | 2
Sexual Function Abnormal
Male | 3 | 1
Female | 2 | 0

Fluvoxamine treatment has been associated with several cases of priapism. In those cases with a known outcome, patients recovered without sequelae and upon discontinuation of fluvoxamine.

While it is difficult to know the precise risk of sexual dysfunction associated with the use of SSRIs, health care providers should routinely inquire about such possible side effects.

6.5 Weight and Vital Sign Changes

No statistically significant differences in weight gain or loss were found between patients treated with fluvoxamine maleate extended-release capsules or placebo. Comparisons of immediate-release fluvoxamine maleate tablets or fluvoxamine maleate extended-release capsules versus placebo groups in separate short-term trials on (1) median change from baseline on various vital signs variables and on (2) incidence of patients meeting criteria for potentially important changes from baseline on various measures of vital signs variables revealed no important differences between fluvoxamine maleate and placebo.

6.6 Laboratory Changes

Comparisons of immediate-release fluvoxamine maleate tablets or fluvoxamine maleate extended-release capsules versus placebo groups in separate short-term trials on (1) median change from baseline on various serum chemistry, hematology, and urinalysis variables and on (2) incidence of patients meeting criteria for potentially important changes from baseline on various serum chemistry, hematology, and urinalysis variables revealed no important differences between fluvoxamine maleate and placebo.

6.7 ECG Changes

Comparisons of immediate-release fluvoxamine maleate tablets or fluvoxamine maleate extended-release capsules and placebo groups in separate pools of short-term OCD and depression trials on (1) mean change from baseline on various ECG variables and on (2) incidence of patients meeting criteria for potentially important changes from baseline on various ECG variables revealed no important differences between fluvoxamine maleate and placebo.

6.8 Other Reactions Observed During the Premarketing Evaluation of Fluvoxamine

During premarketing clinical trials conducted in North America and Europe, multiple doses of fluvoxamine maleate extended-release capsules or immediate-release fluvoxamine maleate tablets were administered for a combined total of 3219 patient exposures in patients suffering OCD or other studied disorders. These exposures include 482 patient exposures with fluvoxamine maleate extended-release capsules and 2737 patient exposures with immediate-release fluvoxamine maleate tablets. Untoward reactions associated with this exposure were recorded by clinical investigators using descriptive terminology of their own choosing. Consequently, it is not possible to provide a meaningful estimate of the proportion of individuals experiencing adverse reactions without first grouping similar types of untoward reactions into a limited (i.e., reduced) number of standard reaction categories.

In the tabulations that follow, a COSTART-based Dictionary terminology has been used to classify reported adverse reactions. If the COSTART term for a reaction was so general as to be uninformative, it was replaced with a more informative term when possible. The frequencies presented, therefore, represent the proportion of the total patient exposures to multiple doses of fluvoxamine maleate who experienced a reaction of the type cited on at least one occasion while receiving fluvoxamine maleate. Reactions are further classified within body system categories and enumerated in order of decreasing frequency using the following definitions: frequent adverse reactions are defined as those occurring on one or more occasions in at least 1/100 patients; infrequent adverse reactions are those occurring between 1/100 and 1/1,000 patients; and rare adverse reactions are those occurring in less than 1/1,000 patients. It is important to emphasize that, although the events reported did occur during treatment with fluvoxamine maleate, a causal relationship to fluvoxamine maleate has not been established.

For fluvoxamine maleate extended-release capsules, all reported events are included in the list below, with the following exclusions: 1) those events already listed in Table 2 or previous sections of this prescribing information; 2) those events for which there is no basis to suspect a causal relationship; and 3) events that were reported in only one patient and judged not to be potentially serious.

Body as a Whole: Infrequent:chills, malaise, photosensitivity reaction, suicide attempt.

Cardiovascular System: Infrequent:syncope.

Digestive System: Infrequent:eructation, increased salivation.

Metabolic and Nutritional Disorders: Frequent:weight gain.

Nervous System: Infrequent:confusion, incoordination, sleep disorder, suicidal tendency.

Skin and Appendages: Infrequent:eczema, urticaria.

Special Senses: Infrequent:dry eyes, photophobia, taste loss.

Urogenital System: Infrequent:vaginal hemorrhage^1.

^1Based on the number of females.

For immediate-release fluvoxamine tablets, all reported events are included in the list below, with the following exclusions: 1) those events already listed in Table 2, in previous sections of this prescribing information, or in the fluvoxamine maleate extended-release capsules list of Other Reactions Observed During Premarketing Evaluation; 2) those events for which there is no basis to suspect a causal relationship; and 3) events that were reported in only one patient and judged not to be potentially serious.

Body as a Whole: Infrequent:allergic reaction, neck pain, neck rigidity, overdose; Rare:sudden death.

Cardiovascular System: Frequent:hypotension; Infrequent:angina pectoris, bradycardia, cardiomyopathy, cardiovascular disease, cold extremities, conduction delay, myocardial infarction, pallor, pulse irregular, ST segment changes; Rare:AV block, cerebrovascular accident, embolus, pericarditis, phlebitis, pulmonary infarction, supraventricular extrasystoles.

Digestive System: Frequent:elevated liver transaminases; Infrequent:colitis, esophagitis, gastritis, gastroenteritis, gastrointestinal hemorrhage, gastrointestinal ulcer, glossitis, hemorrhoids, melena, rectal hemorrhage, stomatitis; Rare:biliary pain, cholecystitis, cholelithiasis, fecal incontinence, hematemesis, intestinal obstruction, jaundice.

Endocrine System: Infrequent:hypothyroidism; Rare:goiter.

Hemic and Lymphatic Systems: Infrequent:leukocytosis, lymphadenopathy, thrombocytopenia; Rare:leukopenia, purpura.

Metabolic and Nutritional Systems: Frequent:edema; Infrequent:dehydration, hypercholesterolemia; Rare:diabetes mellitus, hyperglycemia, hyperlipidemia, hypoglycemia, hypokalemia, lactate dehydrogenase increased.

Musculoskeletal System: Infrequent:arthralgia, arthritis, bursitis, generalized muscle spasm, myasthenia; Rare:myopathy.

Nervous System: Frequent:amnesia, apathy, hyperkinesia, hypokinesia, manic reaction, myoclonus, psychotic reaction; Infrequent:agoraphobia, akathisia, ataxia, CNS depression, convulsion, delirium, delusion, depersonalization, dyskinesia, dystonia, emotional lability, euphoria, extrapyramidal syndrome, gait unsteady, hallucinations, hemiplegia, hostility, hypersomnia, hypochondriasis, hypotonia, hysteria, increased libido, paralysis, paranoid reaction, phobia, psychosis, stupor, twitching, vertigo; Rare:akinesia, coma, fibrillations, mutism, obsessions, reflexes decreased, slurred speech, tardive dyskinesia, torticollis, trismus, withdrawal syndrome.

Respiratory System: Frequent:cough increased, sinusitis; Infrequent:asthma, bronchitis, hoarseness, hyperventilation; Rare:apnea, congestion of upper airway, hemoptysis, hiccups, laryngismus, obstructive pulmonary disease, pneumonia.

Skin: Infrequent:alopecia, dry skin, exfoliative dermatitis, furunculosis, seborrhea, skin discoloration.

Special Senses: Infrequent:accommodation abnormal, conjunctivitis, diplopia, eye pain, mydriasis, otitis media, parosmia, visual field defect; Rare:corneal ulcer.

Urogenital System: Infrequent:anuria, cystitis, delayed menstruation^1, dysuria, female lactation^1, hematuria, menopause^1, metrorrhagia^1, nocturia, premenstrual syndrome^1, urination impaired, vaginitis^1; Rare:kidney calculus, hematospermia^2, oliguria.

^1Based on the number of females.

^2Based on the number of males.

6.9 Postmarketing Reports

The following adverse reactions have been identified during post-approval use of immediate-release fluvoxamine maleate tablets or fluvoxamine maleate extended-release capsules. Because these reactions are reported voluntarily from a population of uncertain size, it is not always possible to reliably estimate their frequency or establish a causal relationship to drug exposure. (Reactions that are discussed in other sections of this prescribing information are not repeated here.) These reactions include: activation syndrome, aggression, agranulocytosis, anaphylactic reaction, anger, blood glucose increased, bruxism, cardio-respiratory arrest, crying, dysarthria, dysphagia, electrocardiogram QT prolonged, fall, fatigue, feeling drunk, feeling jittery, gait disturbance, gastroesophageal reflux disease, glossodynia, hepatitis, homicidal ideation, impulsive behavior, ileus, inappropriate antidiuretic hormone secretion, interstitial lung disease, irritability, loss of consciousness, lethargy, muscular weakness, Parkinsonism, pancreatitis, pyrexia, renal impairment, rhabdomyolysis, self injurious behavior, shock, somnolence neonatal, Stevens-Johnson syndrome, tachycardia, urinary retention, ventricular arrythmia, ventricular tachycardia (including torsades de pointes known to cause cardiac arrest, sometimes fatal), vision blurred, white blood cell count decreased, anosmia, and hyposmia.

To report SUSPECTED ADVERSE REACTIONS, contact AvKARE at 1-855-361-3993; email drugsafety@avkare.com or FDA at 1-800-FDA-1088 or www.fda.gov/medwatch.

7 DRUG INTERACTIONS

7.1 Potential Interactions with Drugs that Inhibit or are Metabolized by Cytochrome P450 Isoenzymes

Multiple hepatic cytochrome P450 isoenzymes are involved in the oxidative biotransformation of a large number of structurally different drugs and endogenous compounds. The available knowledge concerning the relationship of fluvoxamine and the cytochrome P450 isoenzyme system has been obtained mostly from pharmacokinetic interaction studies conducted in healthy volunteers, but some preliminary in vitrodata are also available. Based on a finding of substantial interactions of fluvoxamine with certain of these drugs (see later parts of this section and also Warnings and Precautions [5]for details) and limited in vitrodata for CYP3A4, it appears that fluvoxamine inhibits several cytochrome P450 isoenzymes that are known to be involved in the metabolism of other drugs such as: CYP1A2 (e.g., warfarin, theophylline, propranolol, tizanidine), CYP2C9 (e.g., warfarin), CYP3A4 (e.g., alprazolam), and CYP2C19 (e.g., omeprazole).

In vitrodata suggest that fluvoxamine is a relatively weak inhibitor of CYP2D6.

Approximately 7% of the normal population has a genetic code that leads to reduced levels of activity of CYP2D6 enzyme. Such individuals have been referred to as “poor metabolizers” (PM) of drugs such as debrisoquin, dextromethorphan, and tricyclic antidepressants. While none of the drugs studied for drug interactions significantly affected the pharmacokinetics of fluvoxamine, an in vivostudy of fluvoxamine single-dose pharmacokinetics in 13 PM subjects demonstrated altered pharmacokinetic properties compared to 16 “extensive metabolizers” (EM): mean Cmax, AUC, and half-life were increased by 52%, 200%, and 62%, respectively, in the PM compared to the EM group. This suggests that fluvoxamine is metabolized, at least in part, by CYP2D6. Caution is indicated in patients known to have reduced levels of cytochrome P450 2D6 activity and those receiving concomitant drugs known to inhibit this cytochrome P450 isoenzyme (e.g., quinidine).

The metabolism of fluvoxamine has not been fully characterized and the effects of potent cytochrome P450 isoenzyme inhibition, such as the ketoconazole inhibition of CYP3A4, on fluvoxamine metabolism have not been studied.

A clinically significant fluvoxamine interaction is possible with drugs having a narrow therapeutic ratio such as pimozide, warfarin, theophylline, certain benzodiazepines, omeprazole, and phenytoin. If fluvoxamine maleate extended-release capsules are to be administered together with a drug that is eliminated via oxidative metabolism and has a narrow therapeutic window, plasma levels and/or pharmacodynamic effects of the latter drug should be monitored closely, at least until steady-state conditions are reached (see Contraindications [4] and Warnings and Precautions [5]).

7.2 CNS Active Drugs

Antipsychotics: See Warnings and Precautions (5.2).

Benzodiazepines: See Warnings and Precautions (5.9).

Alprazolam: See Warnings and Precautions (5.9).

Diazepam: See Warnings and Precautions (5.9).

Lorazepam:A study of multiple doses of immediate-release fluvoxamine maleate tablets (50 mg given twice daily) in healthy male volunteers (N=12) and a single dose of lorazepam (4 mg single dose) indicated no significant pharmacokinetic interaction. On average, both lorazepam alone and lorazepam with fluvoxamine produced substantial decrements in cognitive functioning; however, the coadministration of fluvoxamine and lorazepam did not produce larger mean decrements compared to lorazepam alone.

Alcohol:Studies involving single 40 g doses of ethanol (oral administration in one study and intravenous in the other) and multiple dosing with immediate-release fluvoxamine maleate tablets (50 mg given twice daily) revealed no effect of either drug on the pharmacokinetics or pharmacodynamics of the other. As with other psychotropic medications, patients should be advised to avoid alcohol while taking fluvoxamine maleate extended-release capsules.

Carbamazepine:Elevated carbamazepine levels and symptoms of toxicity have been reported with the coadministration of immediate-release fluvoxamine maleate tablets and carbamazepine.

Clozapine: See Warnings and Precautions (5.9).

Lithium:As with other serotonergic drugs, lithium may enhance the serotonergic effects of fluvoxamine and, therefore, the combination should be used with caution. Seizures have been reported with the coadministration of immediate-release fluvoxamine maleate tablets and lithium.

Methadone: See Warnings and Precautions (5.9).

Monoamine Oxidase Inhibitors: See Contraindications (4.1) and Warnings and Precautions (5.2).

Pimozide: See Contraindications (4) and Warnings and Precautions (5.6).

Ramelteon: See Contraindications (4) and Warnings and Precautions (5.8).

Serotonergic Drugs: See Warnings and Precautions (5.2).

Tacrine:In a study of 13 healthy, male volunteers, a single 40 mg dose of tacrine added to immediate-release fluvoxamine maleate tablets 100 mg/day administered at steady-state was associated with 5- and 8-fold increases in tacrine Cmaxand AUC, respectively, compared to the administration of tacrine alone. Five subjects experienced nausea, vomiting, sweating, and diarrhea following coadministration, consistent with the cholinergic effects of tacrine.

Thioridazine: See Contraindications (4) and Warnings and Precautions (5.4).

Tizanidine: See Contraindications (4) and Warnings and Precautions (5.5).

Tricyclic Antidepressants (TCAs):Significantly increased plasma TCA levels have been reported with the coadministration of immediate-release fluvoxamine maleate tablets and amitriptyline, clomipramine or imipramine. Caution is indicated with the coadministration of fluvoxamine maleate extended-release capsules and TCAs; plasma TCA concentrations may need to be monitored, and the dose of TCA may need to be reduced.

Triptans:There have been rare postmarketing reports of serotonin syndrome with use of an SSRI and a triptan. If concomitant treatment of fluvoxamine maleate extended-release capsules with a triptan is clinically warranted, careful observation of the patient is advised, particularly during treatment initiation and dose increases (see Warnings and Precautions [5.2]) .

Sumatriptan-There have been rare postmarketing reports describing patients with weakness, hyperreflexia, and incoordination following the use of a selective serotonin reuptake inhibitor (SSRI) and sumatriptan. If concomitant treatment with sumatriptan and an SSRI (e.g., fluoxetine, fluvoxamine, paroxetine, sertraline) is clinically warranted, appropriate observation of the patient is advised.

Tryptophan:Tryptophan may enhance the serotonergic effects of fluvoxamine, and the combination should, therefore, be used with caution. Severe vomiting has been reported with the coadministration of immediate-release fluvoxamine maleate tablets and tryptophan (see Warnings and Precautions [5.2]) .

7.3 Other Drugs

Alosetron: See Contraindications (4), Warnings and Precautions (5.7), and Lotronex®(alosetron) package insert.

Digoxin:Administration of immediate-release fluvoxamine maleate tablets 100 mg daily for 18 days (N=8) did not significantly affect the pharmacokinetics of a 1.25 mg single intravenous dose of digoxin.

Diltiazem:Bradycardia has been reported with the coadministration of immediate-release fluvoxamine maleate tablets and diltiazem.

Mexiletine: See Warnings and Precautions (5.9).

Propranolol and Other Beta-Blockers:Coadministration of immediate-release fluvoxamine maleate tablets 100 mg per day and propranolol 160 mg per day in normal volunteers resulted in a mean five-fold increase (range 2 to 17) in minimum propranolol plasma concentrations. In this study, there was a slight potentiation of the propranolol-induced reduction in heart rate and reduction in the exercise diastolic pressure.

One case of bradycardia and hypotension and a second case of orthostatic hypotension have been reported with the coadministration of immediate-release fluvoxamine maleate tablets and metoprolol.

If propranolol or metoprolol is coadministered with fluvoxamine maleate extended-release capsules, a reduction in the initial beta-blocker dose and more cautious dose titration are recommended. No dosage adjustment is required for fluvoxamine maleate extended-release capsules.

Coadministration of immediate-release fluvoxamine maleate tablets 100 mg per day with atenolol 100 mg per day (N=6) did not affect the plasma concentrations of atenolol. Unlike propranolol and metoprolol, which undergo hepatic metabolism, atenolol is eliminated primarily by renal excretion.

Theophylline: See Warnings and Precautions (5.9).

Warfarin and Other Drugs that Interfere with Hemostasis (NSAIDs, Aspirin, etc.): See Warnings and Precautions (5.9, 5.11).

7.4 Effects of Smoking on Fluvoxamine Metabolism

Smokers had a 25% increase in the metabolism of fluvoxamine compared to nonsmokers.

7.5 Electroconvulsive Therapy (ECT)

There are no clinical studies establishing the benefits or risks of combined use of ECT and fluvoxamine maleate.

7.6 Monoamine Oxidase Inhibitors (MAOIs)

See Dosage and Administration (2.6, 2.7), Contraindications (4.1), Warnings and Precautions (5.2).

7.7 Serotonergic Drugs

See Dosage and Administration (2.6, 2.7), Contraindications (4.1), Warnings and Precautions (5.2).

8 USE IN SPECIFIC POPULATIONS

8.1 Pregnancy

Teratogenic Effects:When pregnant rats were given daily doses of fluvoxamine (60 mg/kg, 120 mg/kg, or 240 mg/kg) orally throughout the period of organogenesis, developmental toxicity in the form of increased embryofetal death and increased incidences of fetal eye abnormalities (folded retinas) was observed at doses of 120 mg/kg or greater. Decreased fetal body weight was seen at the high dose. The no effect dose for developmental toxicity in this study was 60 mg/kg (approximately 2 times the maximum recommended human dose [MRHD] on a mg/m^2basis).

In a study in which pregnant rabbits were administered doses of up to 40 mg/kg (approximately 2 times the MRHD on a mg/m^2basis) orally during organogenesis, no adverse effects on embryofetal development were observed.

In other reproduction studies in which female rats were dosed orally during pregnancy and lactation (5 mg/kg, 20 mg/kg, 80 mg/kg, or 160 mg/kg), increased pup mortality at birth was seen at doses of 80 mg/kg or greater and decreases in pup body weight and survival were observed at all doses (low effect dose approximately 0.1 times the MRHD on a mg/m^2basis).

Nonteratogenic Effects: Based on data from published observational studies, exposure to SSRIs, particularly in the month before delivery, has been associated with a less than 2-fold increase in the risk of postpartum hemorrhage [see Warnings and Precautions (5.11) and Clinical Considerations] . Neonates exposed to fluvoxamine maleate tablets and other SSRIs or serotonin and norepinephrine reuptake inhibitors (SNRIs) late in the third trimester have developed complications requiring prolonged hospitalization, respiratory support, and tube feeding. Such complications can arise immediately upon delivery. Reported clinical findings have included respiratory distress, cyanosis, apnea, seizures, temperature instability, feeding difficulty, vomiting, hypoglycemia, hypotonia, hypertonia, hyperreflexia, tremor, jitteriness, irritability and constant crying. These features are consistent with either a direct toxic effect of SSRIs or SNRIs or, possibly, a drug discontinuation syndrome. It should be noted that, in some cases, the clinical picture is consistent with serotonin syndrome (see Warnings and Precautions-Serotonin Syndrome [5.2]) .

Infants exposed to SSRIs in pregnancy may have an increased risk for persistent pulmonary hypertension of the newborn (PPHN). PPHN occurs in 1 to 2 per 1,000 live births in the general population and is associated with substantial neonatal morbidity and mortality. Several recent epidemiologic studies suggest a positive statistical association between SSRI use (fluvoxamine maleate and fluvoxamine maleate extended-release are SSRIs) in pregnancy and PPHN. Other studies do not show a significant statistical association.

Physicians should also note the results of a prospective longitudinal study of 201 pregnant women with a history of major depression, who were either on antidepressants or had received antidepressants less than 12 weeks prior to their last menstrual period, and were in remission. Women who discontinued antidepressant medication during pregnancy showed a significant increase in relapse of their major depression compared to those women who remained on antidepressant medication throughout pregnancy.

When treating a pregnant woman with fluvoxamine, the physician should carefully consider both the potential risks of taking an SSRI, along with the established benefits of treating depression with an antidepressant. This decision can only be made on a case by case basis (see Dosage and Administration [2.7]).

Maternal Adverse Reactions: Use of fluvoxamine maleate extended-release capsules in the month before delivery may be associated with an increased risk of postpartum hemorrhage [see Warnings and Precautions (5.11)].

8.2 Labor and Delivery

The effect of fluvoxamine on labor and delivery in humans is unknown.

8.3 Nursing Mothers

Fluvoxamine is secreted in human breast milk. Because of the potential for serious adverse reactions in nursing infants from fluvoxamine maleate extended-release capsules, a decision should be made whether to discontinue nursing or discontinue the drug, taking into account the importance of the drug to the mother.

8.4 Pediatric Use

Fluvoxamine maleate extended-release capsules have not been evaluated in pediatric patients (see BOXED WARNING). The efficacy of fluvoxamine maleate administered as immediate-release tablets for the treatment of OCD was demonstrated in a 10-week multicenter placebo-controlled study with 120 outpatients ages 8 to 17. In addition, 99 of these outpatients continued open-label fluvoxamine maleate treatment for up to another one to three years, equivalent to 94 patient years. The adverse reaction profile observed in that study was generally similar to that observed in adult studies with immediate-release fluvoxamine maleate tablets (see Adverse Reactions [6.3]) .

Decreased appetite and weight loss have been observed in association with the use of fluvoxamine as well as other SSRIs. Consequently, regular monitoring of weight and growth should be performed in children and adolescents treated with an SSRI such as fluvoxamine maleate extended-release capsules.

The risks, if any, that may be associated with fluvoxamine’s extended use in children and adolescents with OCD have not been systematically assessed. The prescriber should be mindful that the evidence relied upon to conclude that fluvoxamine is safe for use in children and adolescents derives from relatively short-term clinical studies and from extrapolation of experience gained with adult patients. In particular, there are no studies that directly evaluate the effects of long-term fluvoxamine use on the growth, cognitive behavioral development, and maturation of children and adolescents. Although there is no affirmative finding to suggest that fluvoxamine possesses a capacity to adversely affect growth, development, or maturation, the absence of such findings is not compelling evidence of the absence of the potential of fluvoxamine to have adverse effects in chronic use (see Warnings and Precautions –Clinical Worsening and Suicide Risk [5.1]) .

Safety and effectiveness in the pediatric population other than pediatric patients with OCD have not been established (see BOXED WARNING and Warnings and Precautions–Clinical Worsening and Suicide Risk [5.1]) . Anyone considering the use of fluvoxamine maleate extended-release capsules in a child or adolescent must balance the potential risks with the clinical need.

8.5 Geriatric Use

Approximately 230 patients and 5 patients participating in controlled premarketing studies with immediate-release fluvoxamine maleate tablets and fluvoxamine maleate extended-release capsules, respectively, were 65-years of age or over. No overall differences in safety were observed between these patients and younger patients. Other reported clinical experience has not identified differences in response between the elderly and younger patients. However, SSRIs and SNRIs, including fluvoxamine, have been associated with several cases of clinically significant hyponatremia in elderly patients, who may be at greater risk for this adverse reaction (see Warnings and Precautions [5.14]) . Furthermore, the clearance of fluvoxamine is decreased by about 50% in elderly compared to younger patients (see Clinical Pharmacology–Elderly [12.3]) , and greater sensitivity of some older individuals also cannot be ruled out. Consequently, a lower starting dose should be considered in elderly patients, and fluvoxamine maleate extended-release capsules should be slowly titrated during initiation of therapy.

9 DRUG ABUSE AND DEPENDENCE

9.1 Controlled Substance Class

Fluvoxamine maleate extended-release capsules are not a controlled substance.

9.2 Physical and Psychological Dependence

The potential for abuse, tolerance, and physical dependence with immediate-release fluvoxamine maleate has been studied in a nonhuman primate model. No evidence of dependency phenomena was found. The discontinuation effects of fluvoxamine maleate extended-release capsules were not systematically evaluated in controlled clinical trials. Fluvoxamine maleate extended-release capsules were not systematically studied in clinical trials for potential for abuse, but there was no indication of drug-seeking behavior in clinical trials. It should be noted, however, that patients at risk for drug dependency were systematically excluded from investigational studies of immediate-release fluvoxamine maleate. Generally, it is not possible to predict on the basis of preclinical or premarketing clinical experience the extent to which a CNS active drug will be misused, diverted, and/or abused once marketed. Consequently, health care providers should carefully evaluate patients for a history of drug abuse and follow such patients closely, observing them for signs of fluvoxamine maleate extended-release capsules misuse or abuse (i.e., development of tolerance, incrementation of dose, drug-seeking behavior).

10 OVERDOSAGE

10.1 Human Experience

Exposure to immediate-release fluvoxamine maleate tablets includes over 45,000 patients treated in clinical trials and an estimated exposure of 50,000,000 patients treated during worldwide marketing experience (end of 2005). Of the 539 cases of deliberate or accidental overdose involving fluvoxamine reported from this population, there were 55 deaths. Of these, 9 were in patients thought to be taking immediate-release fluvoxamine tablets alone and the remaining 46 were in patients taking fluvoxamine along with other drugs. Among non-fatal overdose cases, 404 patients recovered completely. Five patients experienced adverse sequelae of overdosage, to include persistent mydriasis, unsteady gait, hypoxic encephalopathy, kidney complications (from trauma associated with overdose), bowel infarction requiring a hemicolectomy, and vegetative state. In 13 patients, the outcome was provided as abating at the time of reporting. In the remaining 62 patients, the outcome was unknown. The largest known ingestion of fluvoxamine immediate-release tablets involved 12,000 mg (equivalent to 2 to 3 months' dosage). The patient fully recovered. However, ingestions as low as 1,400 mg have been associated with lethal outcome, indicating considerable prognostic variability.

In the controlled clinical trials with 403 patients treated with fluvoxamine maleate extended-release capsules, there was one nonfatal intentional overdose.

Commonly (greater than or equal to 5%) observed adverse reactions associated with fluvoxamine maleate overdose include gastrointestinal complaints (nausea, vomiting, and diarrhea), coma, hypokalemia, hypotension, respiratory difficulties, somnolence, and tachycardia. Other notable signs and symptoms seen with immediate-release fluvoxamine maleate overdose (single or multiple drugs) include bradycardia, ECG abnormalities (such as heart arrest, QT interval prolongation, first degree atrioventricular block, bundle branch block, and junctional rhythm), convulsions, dizziness, liver function disturbances, tremor, and increased reflexes.

10.2 Management of Overdosage

Treatment should consist of those general measures employed in the management of overdosage with any antidepressant.

Ensure an adequate airway, oxygenation, and ventilation. Monitor cardiac rhythm and vital signs. General supportive and symptomatic measures are also recommended. Induction of emesis is not recommended. Gastric lavage with a large-bore orogastric tube with appropriate airway protection, if needed, may be indicated if performed soon after ingestion, or in symptomatic patients.

Activated charcoal should be administered. Due to the large volume of distribution of this drug, forced diuresis, dialysis, hemoperfusion, and exchange transfusion are unlikely to be of benefit. No specific antidotes for fluvoxamine are known.

A specific caution involves patients taking, or recently having taken, fluvoxamine maleate who might ingest excessive quantities of a tricyclic antidepressant. In such a case, accumulation of the parent tricyclic and/or an active metabolite may increase the possibility of clinically significant sequelae and extend the time needed for close medical observation (see Drug Interactions [7.2]) .

In managing overdosage, consider the possibility of multiple drug involvement. The health care provider should consider contacting a poison control center for additional information on the treatment of any overdose. Telephone numbers for certified poison control centers are listed in the Physicians’ Desk Reference (PDR).

11 DESCRIPTION

Fluvoxamine maleate extended-release capsules, for oral administration, contain fluvoxamine maleate USP, a selective serotonin (5-HT) reuptake inhibitor (SSRI) belonging to the chemical series, the 2-aminoethyl oxime ethers of aralkylketones.

Fluvoxamine maleate, USP is chemically designated as 5-methoxy-4'-(trifluoromethyl) valerophenone-(E)-O-(2-aminoethyl)oxime maleate (1:1) and has the molecular formula C15H21O2N2F3•C4H4O4. Its molecular weight is 434.41.

The structural formula is:

Fluvoxamine maleate, USP is a white to off-white, odorless, crystalline powder that is sparingly soluble in water, freely soluble in ethanol and chloroform, and practically insoluble in diethyl ether.

Fluvoxamine maleate extended-release capsules are available in 100 mg and 150 mg strengths for oral administration. In addition to the active ingredient, fluvoxamine maleate USP, each capsule contains the following inactive ingredients: ammonio methacrylate copolymer, type A, ammonio methacrylate copolymer, type B, black iron oxide, FD&C Blue #1, gelatin, hydroxypropyl cellulose, sodium lauryl sulfate, sugar spheres (which contain sucrose and corn starch), talc, titanium dioxide, triethyl citrate, yellow iron oxide. The capsules are imprinted with black Tek-Print ink SW-9008 and SW-9009 which contain black iron oxide, potassium hydroxide, propylene glycol and shellac.

12 CLINICAL PHARMACOLOGY

12.1 Mechanism of Action

The mechanism of action of fluvoxamine maleate in obsessive compulsive disorder is presumed to be linked to its specific serotonin reuptake inhibition in brain neurons. Fluvoxamine has been shown to be a potent inhibitor of the serotonin reuptake transporter in preclinical studies, both in vitroand in vivo.

12.2 Pharmacodynamics

In in vitrostudies, fluvoxamine maleate had no significant affinity for histaminergic, alpha or beta adrenergic, muscarinic, or dopaminergic receptors. Antagonism of some of these receptors is thought to be associated with various sedative, cardiovascular, anticholinergic, and extrapyramidal effects of some psychotropic drugs.

12.3 Pharmacokinetics

Bioavailability:A single-dose crossover study in 28 healthy subjects was conducted to compare the pharmacokinetics of fluvoxamine after administration of fluvoxamine maleate extended-release capsules and immediate-release fluvoxamine maleate tablets.

In the single-dose crossover study, mean Cmaxwas 38% lower and relative bioavailability was 84% for fluvoxamine maleate extended-release capsules versus immediate-release fluvoxamine maleate tablets.

In a multiple-dose proportionality study, fluvoxamine maleate extended-release capsules were administered over a dose range of 100 mg/day to 300 mg/day to 20 healthy volunteers. Steady-state plasma concentrations were achieved within a week of dosing. Mean maximum plasma concentrations were 47 ng/mL, 161 ng/mL, and 319 ng/mL, respectively, at the 100 mg, 200 mg, and 300 mg administered dose levels. Fluvoxamine exhibited nonlinear pharmacokinetics producing disproportionately higher concentrations over the dose range. The AUC and Cmaxvalues increased 5.7-fold following the 3-fold increase in dose from 100 mg to 300 mg.

Food caused the mean AUC and Cmaxof fluvoxamine to increase only slightly; therefore, administration of fluvoxamine maleate extended-release capsules with food does not significantly affect the absorption of fluvoxamine.

Distribution/Protein Binding:The mean apparent volume of distribution for fluvoxamine is approximately 25 L/kg, suggesting extensive tissue distribution.

Approximately 80% of fluvoxamine is bound to plasma protein, mostly albumin, over a concentration range of 20 to 2,000 ng/mL.

Metabolism:Fluvoxamine maleate is extensively metabolized by the liver; the main metabolic routes are oxidative demethylation and deamination. Nine metabolites were identified following a 5 mg radiolabelled dose of fluvoxamine maleate, constituting approximately 85% of the urinary excretion products of fluvoxamine. The main human metabolite was fluvoxamine acid which, together with its N-acetylated analog, accounted for about 60% of the urinary excretion products. A third metabolite, fluvoxethanol, formed by oxidative deamination, accounted for about 10%. Fluvoxamine acid and fluvoxethanol were tested in an in vitroassay of serotonin and norepinephrine reuptake inhibition in rats; they were inactive except for a weak effect of the former metabolite on inhibition of serotonin uptake (1 to 2 orders of magnitude less potent than the parent compound). Approximately 2% of fluvoxamine was excreted in urine unchanged (see Drug Interactions [7]) .

Elimination:Following a^14C-labelled oral dose of fluvoxamine maleate (5 mg), an average of 94% of drug-related products was recovered in the urine within 71 hours.

After administration of a 100 mg, single oral dose of fluvoxamine maleate extended-release capsules, the mean plasma half-life of fluvoxamine in healthy male and female volunteers was 16.3 hours.

Gender:In a study with 15 male and 13 female healthy volunteers who were administered fluvoxamine maleate extended-release capsules 100 mg, AUC and Cmaxof fluvoxamine were increased by approximately 60% in females compared to males. There were no differences in the elimination half-life between males and females.

Elderly Subjects:In a study using immediate-release fluvoxamine maleate tablets at 50 mg and 100 mg and comparing elderly (ages 66 to 73 years) and young subjects (ages 19 to 35 years), mean maximum plasma concentrations in the elderly were 40% higher. The multiple-dose elimination half-life of fluvoxamine was 17.4 hours and 25.9 hours in the elderly compared to 13.6 hours and 15.6 hours in the young subjects at steady state for 50 mg and 100 mg doses, respectively.

In elderly patients administered immediate-release fluvoxamine maleate tablets, the clearance of fluvoxamine was reduced by about 50%; therefore, fluvoxamine maleate extended-release capsules should be slowly titrated during initiation of therapy (see Dosage and Administration [2.3]) .

Pediatric Subjects:The pharmacokinetics of fluvoxamine maleate extended-release capsules have not been evaluated in pediatric patients. However, the multiple-dose pharmacokinetics of fluvoxamine were determined in male and female children (ages 6 to 11) and adolescents (ages 12 to 17). Steady-state plasma fluvoxamine concentrations were 2- to 3-fold higher in children than in adolescents. AUC and Cmaxin children were 1.5- to 2.7-fold higher than that in adolescents (see Table 4). As in adults, both children and adolescents exhibited nonlinear multiple-dose pharmacokinetics. Female children showed significantly higher AUC(0-12)and Cmaxcompared to male children and, therefore, lower doses of immediate-release fluvoxamine maleate tablets may produce therapeutic benefit (see Table 5). No gender differences were observed in adolescents. Steady-state plasma fluvoxamine concentrations were similar in adults and adolescents at a dose of 300 mg/day, indicating that fluvoxamine exposure was similar in these two populations (see Table 4). Dose adjustment in adolescents (up to the adult maximum dose of 300 mg) may be indicated to achieve therapeutic benefit.

Table 4: Comparison of Mean (SD) Immediate-Release Tablet Fluvoxamine Maleate Pharmacokinetic Parameters Between Children, Adolescents, and Adults
Pharmacokinetic Parameter | Dose = 200 mg/day |  | Dose = 300 mg/day
(body weight corrected) | (100 mg Twice Daily) |  | (150 mg Twice Daily)
 | Children | Adolescent | Adolescent | Adult
 | (n = 10) | (n = 17) | (n= 13) | (n = 16)
AUC0-12(ng •h/mL/kg) | 155.1 (160.9) | 43.9 (27.9) | 69.6 (46.6) | 59.4 (40.9)
Cmax(ng/mL/kg) | 14.8 (14.9) | 4.2 (2.6) | 6.7 (4.2) | 5.7 (3.9)
Cmin(ng/mL/kg) | 11.0 (11.9) | 2.9 (2.0) | 4.8 (3.8) | 4.6 (3.2)

Table 5: Comparison of Mean (SD) Immediate-Release Tablet Fluvoxamine Maleate Pharmacokinetic Parameters Between Male and Female Children (6 to 11 Years)
 | Dose = 200 mg/day (100 mg Twice Daily)
Pharmacokinetic Parameter (body weight corrected) | Male Children (n = 7) | Female Children (n = 3)
AUC0-12(ng •h/mL/kg) | 95.8 (83.9) | 293.5 (233.0)
Cmax(ng/mL/kg) | 9.1 (7.6) | 28.1 (21.1)
Cmin(ng/mL/kg) | 6.6 (6.1) | 21.2 (17.6)

Hepatic and Renal Disease:A cross-study comparison (healthy subjects versus patients with hepatic dysfunction) using immediate-release fluvoxamine maleate tablets suggested a 30% decrease in fluvoxamine clearance in association with hepatic dysfunction. The mean minimum plasma concentrations in renally impaired patients (creatinine clearance of 5 mL/min to 45 mL/min) after 4 weeks and 6 weeks of treatment (50 mg given twice daily, N = 13) were comparable to each other, suggesting no accumulation of fluvoxamine in these patients (see Warnings and Precautions–Use in Patients with Concomitant Illness [5.15]) .

13 NONCLINICAL TOXICOLOGY

13.1 Carcinogenesis, Mutagenesis, Impairment of Fertility

Carcinogenesis:There was no evidence of carcinogenicity in rats treated orally with fluvoxamine maleate for 30 months or hamsters treated orally with fluvoxamine maleate for 20 months (females) or 26 months (males). The daily doses in the high-dose groups in these studies were increased over the course of the study from a minimum of 160 mg/kg to a maximum of 240 mg/kg in rats, and from a minimum of 135 mg/kg to a maximum of 240 mg/kg in hamsters. The maximum dose of 240 mg/kg is approximately 6 times the maximum recommended human dose (MRHD) on a mg/m^2basis.

Mutagenesis:No evidence of genotoxic potential was observed in a mouse micronucleus test, an in vitrochromosome aberration test, or the Ames microbial mutagen test with or without metabolic activation.

Impairment of Fertility:In a study in which male and female rats were administered fluvoxamine (60, 120, or 240 mg/kg) orally prior to and during mating and gestation, fertility was impaired at doses of 120 mg/kg or greater, as evidenced by increased latency to mating, decreased sperm count, decreased epididymal weight, and decreased pregnancy rate. In addition, the numbers of implantations and embryos were decreased at the highest dose. The no effect dose for fertility impairment was 60 mg/kg (approximately 2 times the MRHD on a mg/m^2basis).

14 CLINICAL STUDIES

14.1 Obsessive Compulsive Disorder (OCD)

The effectiveness of fluvoxamine maleate extended-release capsules for the treatment of OCD was demonstrated in a 12-week, multicenter, placebo-controlled study of adult outpatients. Patients in this trial were titrated in 50 mg increments over the first six weeks of the study on the basis of response and tolerance from a dose of 100 mg/day to a fluvoxamine maleate dose within a range of 100 mg to 300 mg once-a-day. Patients in this study had moderate to severe OCD (DSM-IV), with mean baseline ratings on the Yale-Brown Obsessive Compulsive Scale (Y-BOCS), total scores of 26.6 and 26.3 for fluvoxamine and placebo-treatment groups, respectively.

Patients receiving fluvoxamine maleate extended-release capsules demonstrated statistically significant improvement over placebo patients at the primary endpoint (Week 12) compared to baseline on the Y-BOCS. The mean daily dose of fluvoxamine maleate extended-release capsules administered to patients was 261 mg at end of study.

Exploratory analyses for age and gender effects on outcomes did not show any significant differential responsiveness on the basis of age or sex.

The effectiveness of immediate-release fluvoxamine maleate tablets for the treatment of OCD was demonstrated in two 10-week multicenter, parallel group studies of adult outpatients. Patients in these trials were titrated to a total daily fluvoxamine maleate dose of 150 mg/day over the first two weeks of the trial, after which the dose was adjusted within a range of 100 to 300 mg/day (given in two doses per day), on the basis of response and tolerance. Patients in these studies had moderate to severe OCD (DSM-III-R), with mean baseline ratings on the Yale-Brown Obsessive Compulsive Scale (Y-BOCS) total score of 23.

14.2 Adult OCD Maintenance Study with Immediate-Release Fluvoxamine Maleate Tablets

In a maintenance trial of adult outpatients with OCD, 114 patients meeting DSM-IV criteria for OCD and with a Yale-Brown Obsessive Compulsive Scale (Y-BOCS) score greater than or equal to 18 were titrated to an effective dose of immediate-release fluvoxamine maleate tablets 100 to 300 mg/day as part of an initial 10-week single-blind treatment phase. Treatment response during this single-blind phase was defined as Y-BOCS scores at least 30% lower than baseline at the end of weeks 8 and 10. Of the patients who responded, their average duration of response was 4 weeks. Patients who responded during this initial phase were randomized either to continuation of immediate-release fluvoxamine maleate tablets (N=56) or to placebo (N=58) in a double-blind phase for observation of relapse. Relapse during the double-blind phase was defined as an increase in the Y-BOCS score of at least 30% over the baseline for that phase or patient refusal to continue treatment due to a substantial increase in OCD symptoms. In the double-blind phase, patients receiving continued immediate-release fluvoxamine maleate tablets treatment experienced, on average, a significantly lower relapse rate than those receiving placebo.

An examination of population subgroups from this trial did not reveal any clear evidence of a differential maintenance effect on the basis of age or gender.

14.3 Pediatric OCD Study

Fluvoxamine maleate extended-release capsules have not been evaluated in pediatric patients. However, the effectiveness of immediate-release fluvoxamine maleate tablets for the treatment of OCD was demonstrated in a 10-week multicenter, parallel group study in a pediatric outpatient population (children and adolescents, ages 8 to 17 years). Patients in this study were titrated to a total daily fluvoxamine dose of approximately 100 mg/day over the first two weeks of the trial, following which the dose was adjusted within a range of 50 to 200 mg/day (given in two doses per day) on the basis of response and tolerance. All patients had moderate-to-severe OCD (DSM-III-R) with mean baseline ratings on the Children’s Yale-Brown Obsessive Compulsive Scale (CY-BOCS) total score of 24.

Post hoc exploratory analyses for gender effects on outcomes did not suggest any differential responsiveness on the basis of gender. Further exploratory analyses revealed a prominent treatment effect in the 8 year to 11 year age group and essentially no effect in the 12 year to 17 year age group. While the significance of these results is not clear, the 2 to 3 fold higher steady-state plasma fluvoxamine concentrations in children compared to adolescents (see Clinical Pharmacology–Pediatric Subjects [12.3]) is suggestive that decreased exposure in adolescents may have been a factor, and dose adjustment in adolescents (up to the adult maximum dose of 300 mg/day) may be indicated to achieve therapeutic benefit.

16 HOW SUPPLIED/STORAGE AND HANDLING

16.1 How Supplied

Fluvoxamine maleate extended-release capsules are available as follows:

100 mg – Each #2 capsule with olive opaque cap and gray opaque body, imprinted with and 2848 on both cap and body in black ink contains 100 mg of fluvoxamine maleate, USP. Capsules are supplied in bottles of 30 (NDC 73190-066-30).

150 mg – Each #1 capsule with olive opaque cap and white opaque body, imprinted with and 2849 on both cap and body in black ink contains 150 mg of fluvoxamine maleate, USP. Capsules are supplied in bottles of 30 (NDC 73190-067-30).

16.2 Storage

Keep out of reach of children.

Store at 25°C (77°F); excursions permitted to 15° to 30°C (59° to 86°F) [see USP Controlled Room Temperature].

Protect from high humidity and avoid exposure to temperatures above 30°C (86°F).

Dispense in tight, light-resistant container as defined in the USP.

17 PATIENT COUNSELING INFORMATION

Advise the patient to read the FDA-approved patient labeling (Medication Guide).

Sexual Dysfunction

Advise patients that use of fluvoxamine maleate extended-release capsules may cause symptoms of sexual dysfunction in both male and female patients. Inform patients that they should discuss any changes in sexual function and potential management strategies with their healthcare provider [see Warningsand Precautions (5.17)].

Prescribers or other health professionals should inform patients, their families, and their caregivers about the benefits and risks associated with treatment with fluvoxamine maleate extended-release capsules and should counsel them in the appropriate use. A patient Medication Guide discussing antidepressant medicines, depression and other serious mental illnesses, and suicidal thoughts or actions and other important information about Fluvoxamine Maleate Extended-Release Capsules is available for fluvoxamine maleate extended-release capsules. The prescriber or health professional should instruct patients, their families, and their caregivers to read both sections of the Medication Guide and should assist them in understanding its contents. Patients should be given the opportunity to discuss the contents of the Medication Guide and to obtain answers to any questions they may have. The complete text of the Medication Guide is reprinted at the end of this document.

Patients should be advised of the following issues and asked to alert their prescriber if these occur while taking fluvoxamine maleate extended-release capsules.

Clinical Worsening and Suicide Risk

Patients, their families, and their caregivers should be encouraged to be alert to the emergence of anxiety, agitation, panic attacks, insomnia, irritability, hostility, aggressiveness, impulsivity, akathisia (psychomotor restlessness), hypomania, mania, other unusual changes in behavior, worsening of depression, and suicidal ideation, especially early during antidepressant treatment and when the dose is adjusted up or down. Families and caregivers of patients should be advised to look for the emergence of such symptoms on a day-to-day basis, since changes may be abrupt. Such symptoms should be reported to the patient’s prescriber or health professional, especially if they are severe, abrupt in onset, or were not part of the patient’s presenting symptoms. Symptoms such as these may be associated with an increased risk for suicidal thinking and behavior and indicate the need for very close monitoring and possibly changes in the medication (see BOXED WARNING and Warnings and Precautions [5.1]) .

Serotonin Syndrome

Patients should be cautioned about the risk of serotonin syndrome particularly with the concomitant use of fluvoxamine with other serotonergic agents (including triptans, tricyclic antidepressants, opioids, lithium, tryptophan, buspirone, amphetamines, and St. John’s Wort) [see Warnings and Precautions-Serotonin Syndrome (5.2)].

Contraindicated Medications

Patients should be advised that the following medications should not be used while taking fluvoxamine maleate extended-release capsules:

- Monoamine oxidase inhibitors (MAOIs): See Contraindications (4.1)and Warnings and Precautions (5.2).
- Thioridazine: See Contraindications (4) and Warnings and Precautions (5.4).
- Tizanidine: See Contraindications (4) and Warnings and Precautions (5.5).
- Pimozide: See Contraindications (4) and Warnings and Precautions (5.6).
- Alosetron: See Contraindications (4) and Warnings and Precautions (5.7).
- Ramelteon: See Contraindications (4) and Warnings and Precautions (5.8).

In addition, MAOIs should not be taken within 14 days (2 weeks) after stopping fluvoxamine maleate extended-release capsules, and fluvoxamine maleate extended-release capsules should not be taken within two weeks after stopping treatment with an MAOI (see Contraindications [4.1] and Warnings and Precautions [5.2]) .

Other Potentially Hazardous Drug Interactions

Patients should be advised that the use of fluvoxamine maleate extended-release capsules with any of the following medications may produce clinically significant adverse reactions. Patients should inform their physician if they are taking any of these medications before starting treatment with fluvoxamine maleate extended-release capsules. Patients should also inform their physician prior to taking any of these medications while receiving fluvoxamine maleate extended-release capsule therapy.

- Serotonergic drugs, including triptans, tramadol, and tryptophan: See Warnings and Precautions (5.2).
- Antipsychotic agents, including clozapine: See Warnings and Precautions (5.2, 5.9).
- Certain benzodiazepines: See Warnings and Precautions (5.9).
- Methadone: See Warnings and Precautions (5.9).
- Mexiletine: See Warnings and Precautions (5.9).
- Theophylline: See Warnings and Precautions (5.9).
- Warfarin and other drugs that interfere with hemostasis:Patients should be cautioned about the concomitant use of fluvoxamine and NSAIDs, aspirin, or other drugs that affect coagulation since the combined use of psychotropic drugs that interfere with serotonin reuptake and these agents has been associated with an increased risk of bleeding (see Warnings and Precautions [5.9, 5.11]) .
- Diuretics: See Warnings and Precautions (5.14) .

In addition, patients should be advised to notify their physicians if they are taking, or plan to take, any prescription or over-the-counter drugs, since there is a potential for clinically important interactions with fluvoxamine maleate extended-release capsules.

Abnormal Bleeding
Patients should be advised that fluvoxamine maleate extended-release capsules may increase the risk of bleeding events, which have ranged from ecchymoses, hematomas, epistaxis, and petechiae to life-threatening hemorrhages. Concomitant use of aspirin, nonsteroidal anti-inflammatory drugs, warfarin, and other anticoagulants may add to this risk (see Warnings and Precautions [5.9, 5.11]).

Angle Closure Glaucoma
Patients should be advised that taking fluvoxamine maleate extended-release capsules can cause mild pupillary dilation, which in susceptible individuals, can lead to an episode of angle closure glaucoma. Pre-existing glaucoma is almost always open-angle glaucoma because angle closure glaucoma, when diagnosed, can be treated definitively with iridectomy. Open-angle glaucoma is not a risk factor for angle closure glaucoma. Patients may wish to be examined to determine whether they are susceptible to angle closure, and have a prophylactic procedure (e.g., iridectomy), if they are susceptible (see Warnings and Precautions [5.3])

Interference with Cognitive or Motor Performance
Since any psychoactive drug may impair judgment, thinking, or motor skills, patients should be cautioned about operating hazardous machinery, including automobiles, until they are certain that fluvoxamine maleate extended-release capsules therapy does not adversely affect their ability to engage in such activities.

Pregnancy
Patients should be advised to notify their physicians if they become pregnant or intend to become pregnant during therapy with fluvoxamine maleate extended-release capsules (see Use in Specific Populations [8.1]) .

Nursing
Patients receiving fluvoxamine maleate extended-release capsules should be advised to notify their physicians if they are breastfeeding an infant. (See Use in Specific Populations–Nursing Mothers [8.3]) .

Alcohol
As with other psychotropic medications, patients should be advised to avoid alcohol while taking fluvoxamine maleate extended-release capsules.

Allergic Reactions
Patients should be advised to notify their physicians if they develop a rash, hives, or a related allergic phenomenon during therapy with fluvoxamine maleate extended-release capsules.

Brands listed are the trademarks of their respective owners.

Manufactured For:
AvKARE
Pulaski, TN 38478

AV 11/25 (M)
Mfg.Rev. 05/25

MEDICATION GUIDE
Fluvoxamine Maleate (floo vox' a meen mal' ee ate)
Extended-Release Capsules

Read the Medication Guide that comes with fluvoxamine maleate extended-release capsules before you start taking it and each time you get a refill. There may be new information. This Medication Guide does not take the place of talking to your healthcare provider about your medical condition or treatment. Talk to your healthcare provider if there is something you do not understand or want to learn more about.

What is the most important information I should know aboutfluvoxamine maleate extended-release capsules?

Fluvoxamine maleate extended-release is the same kind of medicine as those used to treat depression. These medicines may cause serious side effects, including:

1. Suicidal thoughts or actions:

- Fluvoxamine maleate extended-release capsules and other antidepressant medicines may increase suicidal thoughts or actionsin some children, teenagers, or young adults within the first few months of treatment or when the dose is changed.
- Depression or other serious mental illnesses are the most important causes of suicidal thoughts or actions.
- Watch for these changes and call your healthcare provider right away if you notice:
- New or sudden changes in mood, behavior, actions, thoughts, or feelings, especially if severe.
- Pay particular attention to such changes when fluvoxamine maleate extended-release is started or when the dose is changed.

Keep all follow-up visits with your healthcare provider and call between visits if you are worried about symptoms.

Call your healthcare provider right away if you have any of the following symptoms, or call 911 in an emergency, especially if they are new, worse, or worry you:

- attempts to commit suicide
- acting on dangerous impulses
- acting aggressive or violent
- thoughts about suicide or dying
- new or worse depression
- new or worse anxiety or panic attacks
- feeling agitated, restless, angry or irritable
- trouble sleeping
- an increase in activity or talking more than what is normal for you
- other unusual changes in behavior or mood

Call your healthcare provider right away if you have any of the following symptoms, or call 911 in an emergency. Fluvoxamine maleate extended-release capsulesmay be associated with these serious side effects:

2. Serotonin Syndrome. This condition can be life-threatening and may include:

- agitation, hallucinations, coma or other changes in mental status
- coordination problems or muscle twitching (overactive reflexes)
- racing heartbeat, high or low blood pressure
- sweating or fever
- nausea, vomiting, or diarrhea
- muscle rigidity

3. Visual Problems

- eye pain
- changes in vision
- swelling or redness in or around the eye

Only some people are at risk for these problems. You may want to undergo an eye examination to see if you are at risk and receive preventative treatment if you are.

4. Severe allergic reactions:

- trouble breathing
- swelling of the face, tongue, eyes, or mouth
- rash, itchy welts (hives) or blisters, alone or with fever or joint pain

5. Abnormal bleeding:Fluvoxamine maleate extended-release capsules and other antidepressant medicines may increase your risk of bleeding or bruising, especially if you take the blood thinner warfarin (Coumadin®, Jantoven®), a non-steroidal anti-inflammatory drug (NSAIDs, like ibuprofen or naproxen), or aspirin.

6. Seizures or convulsions

7. Manic episodes:

- greatly increased energy
- severe trouble sleeping
- racing thoughts
- reckless behavior
- unusually grand ideas
- excessive happiness or irritability
- talking more or faster than usual

8. Changes in appetite or weight.Children and adolescents should have height and weight monitored during treatment.

9. Low salt (sodium) levels in the blood.

Elderly people may be at greater risk for this.

Symptoms may include:

- headache
- weakness or feeling unsteady
- confusion, problems concentrating or thinking, or memory problems

10. Sexual problems (dysfunction).Taking selective serotonin reuptake inhibitors (SSRIs), including fluvoxamine, may cause sexual problems.

Symptoms in males may include:

- Delayed ejaculation or inability to have an ejaculation
- Decreased sex drive
- Problems getting or keeping an erection

Symptoms in females may include:

- Decreased sex drive
- Delayed orgasm or inability to have an orgasm

Talk to your healthcare provider if you develop any changes in your sexual function or if you have any questions or concerns about sexual problems during treatment with fluvoxamine maleate extended-release capsules. There may be treatments your healthcare provider can suggest.

Do not stop takingfluvoxamine maleate extended-release capsules without first talking to your healthcare provider.Stopping fluvoxamine maleate extended-release capsules may cause serious symptoms, including:

- anxiety, irritability, high or low mood, feeling restless or changes in sleep habits
- headache, sweating, nausea, dizziness
- electric shock-like sensations, shaking, confusion

What arefluvoxamine maleate extended-release capsules?

Fluvoxamine maleate extended-release capsules are a prescription medicine used to treat obsessive compulsive disorder (OCD). It is the same kind of drug that is used to treat depression. It is important to talk with your healthcare provider about the risks of treating OCD and also the risks of not treating it. You should discuss all treatment choices with your healthcare provider.

Talk to your healthcare provider if you do not think that your condition is getting better with fluvoxamine maleate extended-release treatment.

Who should not takefluvoxamine maleate extended-release capsules?

Do not take fluvoxamine maleate extended-release capsules if you:

- are allergic to fluvoxamine maleate or any of the ingredients in fluvoxamine maleate extended-release capsules. See the end of this Medication Guide for a complete list of ingredients in fluvoxamine maleate extended-release capsules.
- take a Monoamine Oxidase Inhibitor (MAOI). Ask your healthcare provider or pharmacist if you are not sure if you take an MAOI, including the antibiotic linezolid.
  - Do not take an MAOI within 2 weeks of stopping fluvoxamine maleate extended-release capsules unless directed to do so by your physician.
  - Do not start fluvoxamine maleate extended-release capsules if you stopped taking an MAOI in the last 2 weeks unless directed to do so by your physician.

People who takefluvoxamine maleate extended-release capsules close in time to an MAOI may have serious or even life-threatening side effects. Get medical help right away if you have any of these symptoms:

- high fever
- uncontrolled muscle spasms
- stiff muscles
- rapid changes in heart rate or blood pressure
- confusion
- loss of consciousness (pass out)
- take Mellaril®(thioridazine). Mellaril®should not be taken with fluvoxamine maleate extended-release capsules because this can cause serious heart rhythm problems or sudden death.
- take Zanaflex®(tizanidine) because fluvoxamine maleate extended-release capsules can increase the amount of Zanaflex in your body, which could increase its actions and side effects. This could include causing drowsiness and a drop in blood pressure and affecting how well you do things that require alertness.
- take the antipsychotic medicine Orap®(pimozide) because this can cause serious heart problems.
- Take Lotronex®(alosetron) because fluvoxamine maleate extended-release capsules can increase the amount of Lotronex in your body, which could increase its actions and side effects.
- take Rozerem®(ramelteon) because fluvoxamine maleate extended-release capsules can increase the amount of Rozerem in your body, which could increase its actions and side effects.

What should I tell my healthcare provider before takingfluvoxamine maleate extended-release capsules? Ask if you are not sure.

Before starting fluvoxamine maleate extended-release capsules, tell your healthcare provider if you:

- are taking certain drugs such as:
  - Clozaril®(clozapine): used to treat schizophrenia
  - Mexitil®(mexiletine): used to treat problems with heart rhythm
  - Triptans: used to treat migraine headache
  - Medicines used to treat mood, anxiety, psychotic or thought disorders, including tricyclics, lithium, SSRIs, SNRIs, or antipsychotics
  - Tramadol: used to reduce pain
  - Meperidine
  - Benzodiazepines: used to reduce anxiety, stress, emotional upset, or seizures; helps you sleep; helps with alcohol withdrawal; reduces restlessness; and relaxes muscles
  - Methadone: used to relieve pain or to help with addiction
  - or other opioids
  - Theophylline used to treat swollen air passages in your lungs, to relax the muscles in your chest to ease shortness of breath, often to treat asthma
  - Warfarin and other drugs that affect how your blood clots
  - Diuretics to treat high blood pressure, congestive heart failure, or swelling
  - Over-the-counter supplements such as tryptophan or St. John’s Wort
- have liver problems
- have kidney problems
- have heart problems
- have or had seizures or convulsions
- have bipolar disorder or mania
- have low sodium levels in your blood
- have a history of a stroke
- have high blood pressure
- have or had bleeding problems
- are pregnant or plan to become pregnant. It is not known if fluvoxamine maleate extended-release capsules will harm your unborn baby. Talk to your healthcare provider about the benefits and risks of treating obsessive compulsive disorder (OCD) during pregnancy
- are breastfeeding or plan to breastfeed. Some fluvoxamine maleate may pass into your breast milk. Talk to your healthcare provider about the best way to feed your baby while taking fluvoxamine maleate extended-release capsules.

Tell your healthcare provider about all the medicines that you take,including prescription and non-prescription medicines, vitamins, and herbal supplements. Fluvoxamine maleate extended-release capsules and some medicines may interact with each other, may not work as well, or may cause serious side effects.

Your healthcare provider or pharmacist can tell you if it is safe to take fluvoxamine maleate extended-release capsules with your other medicines. Do not start or stop any medicine while taking fluvoxamine maleate extended-release capsules without talking to your healthcare provider first.

If you take fluvoxamine maleate extended-release capsules, you should not take any other medicines that contain fluvoxamine maleate including: Fluvoxamine Maleate Immediate-Release Tablets.

How should I takefluvoxamine maleate extended-release capsules?

- Take fluvoxamine maleate extended-release capsules at night exactly as prescribed. Your healthcare provider may need to change the dose of fluvoxamine maleate extended-release capsules until it is the right dose for you.
- Fluvoxamine maleate extended-release capsules may be taken with or without food.
- If you miss a dose of fluvoxamine maleate extended-release capsules, take the missed dose as soon as you remember. If it is almost time for the next dose, skip the missed dose and take your next dose at the regular time. Do not take two doses of fluvoxamine maleate extended-release capsules at the same time.
- If you take too much fluvoxamine maleate extended-release, call your healthcare provider or poison control center right away, or get emergency treatment.

What should I avoid while takingfluvoxamine maleate extended-release capsules?

Fluvoxamine maleate extended-release capsules can cause sleepiness or may affect your ability to make decisions, think clearly, or react quickly. You should not drive, operate heavy machinery, or do other dangerous activities until you know how fluvoxamine maleate extended-release capsules affect you. Do not drink alcohol while using fluvoxamine maleate extended-release capsules.

What are the possible side effects offluvoxamine maleate extended-release capsules?

Fluvoxamine maleate extended-release may cause serious side effects, including all of those described in the section entitled “What is the most important information I should know about fluvoxamine maleate extended-release capsules?”

Common possible side effects in people who take fluvoxamine include:

- Nausea
- Sleepiness
- Weakness
- Dizziness
- Feeling anxious
- Trouble sleeping
- Sexual problems
- Sweating
- Shaking
- Not feeling hungry
- Dry mouth
- Diarrhea
- Muscle pain
- Sore throat
- Throwing up
- Upset stomach
- Yawning

Other side effects in children and adolescents taking fluvoxamine include:

- abnormal increase in muscle movement or agitation
- depression
- heavy menstrual periods
- flatulence (gas)
- rash

Tell your healthcare provider if you have any side effect that bothers you or that does not go away. These are not all the possible side effects of fluvoxamine maleate extended-release capsules. For more information, ask your healthcare provider or pharmacist.

CALL YOUR DOCTOR FOR MEDICAL ADVICE ABOUT SIDE EFFECTS. YOU MAY REPORT SIDE EFFECTS TO FDA AT 1-800-FDA-1088.

How should I storefluvoxamine maleate extended-release capsules?

- Store fluvoxamine maleate extended-release capsules at 59°F to 86°F (15°C to 30°C).
- Keep fluvoxamine maleate extended-release capsules away from high temperatures (above 86°F or 30°C) and high humidity (dampness).
- Keep the fluvoxamine maleate extended-release capsules bottle closed tightly.

Keepfluvoxamine maleate extended-release capsules and all medicines out of the reach of children.

General information aboutfluvoxamine maleate extended-release capsules

Medicines are sometimes prescribed for purposes other than those listed in a Medication Guide. Do not use fluvoxamine maleate extended-release capsules for a condition for which they were not prescribed. Do not give fluvoxamine maleate extended-release capsules to other people, even if they have the same condition. It may harm them.

This Medication Guide summarizes the most important information about fluvoxamine maleate extended-release capsules. If you would like more information, talk with your healthcare provider. You may ask your healthcare provider or pharmacist for information about fluvoxamine maleate extended-release capsules that is written for healthcare professionals.

For more information about fluvoxamine maleate extended-release capsules, call AvKARE at 1-888-361-3993.

What are the ingredients influvoxamine maleate extended-release capsules?

Active ingredient:fluvoxamine maleate

Inactive ingredients:ammonio methacrylate copolymer, type A, ammonio methacrylate copolymer, type B, black iron oxide, FD&C Blue #1, gelatin, hydroxypropyl cellulose, sodium lauryl sulfate, sugar spheres (which contain sucrose and corn starch), talc, titanium dioxide, triethyl citrate, yellow iron oxide. The capsules are imprinted with black Tek-Print ink SW-9008 and SW-9009 which contain black iron oxide, potassium hydroxide, propylene glycol and shellac.

Brands listed are the trademarks of their respective owners.

This Medication Guide has been approved by the U.S. Food and Drug Administration.

Manufactured For:
AvKARE
Pulaski, TN 38478

AV 11/25 (M)
Mfg.Rev. 05/25